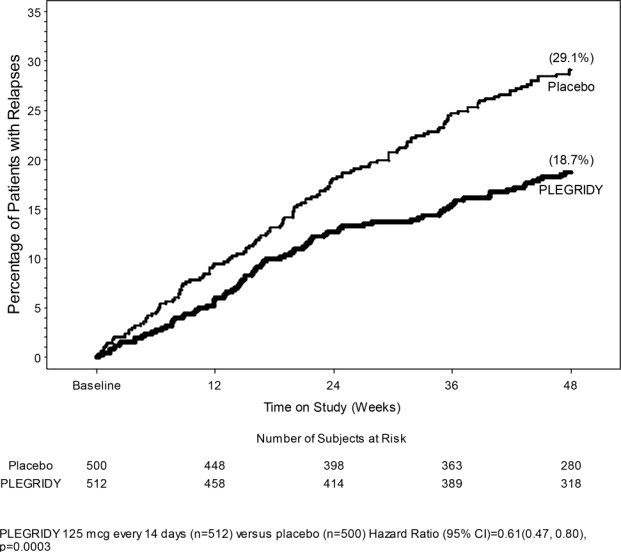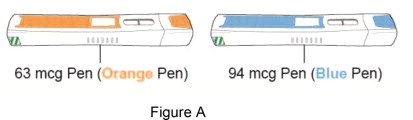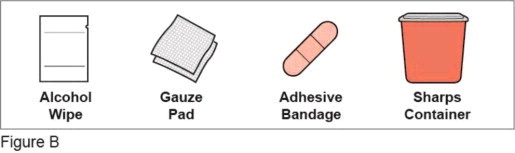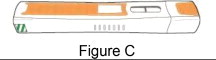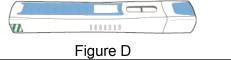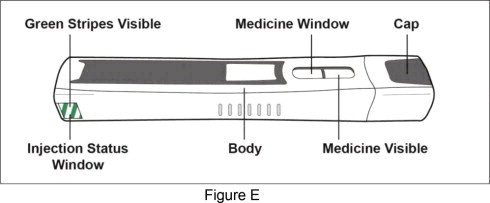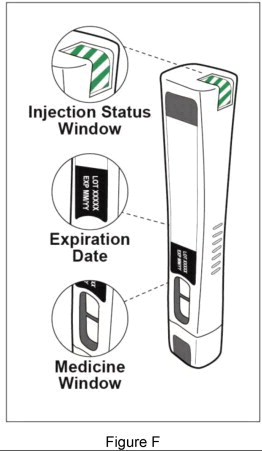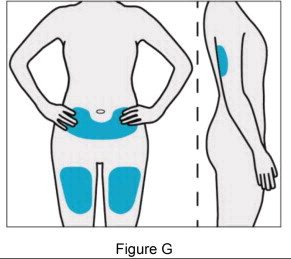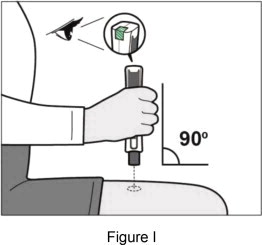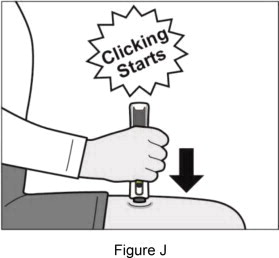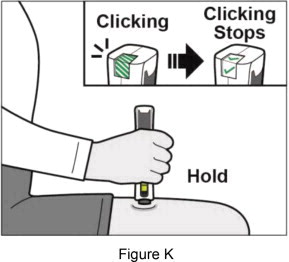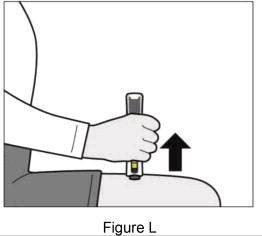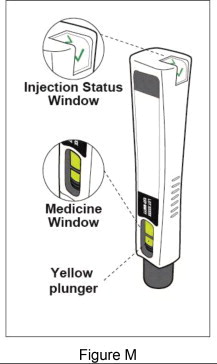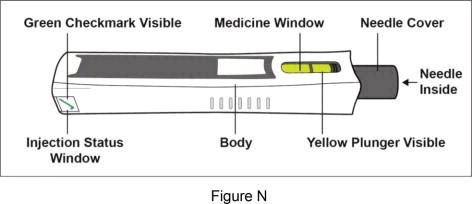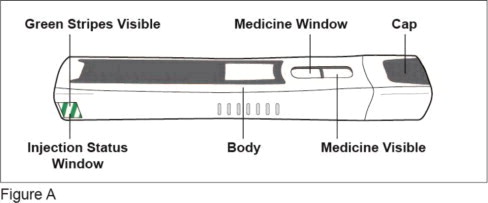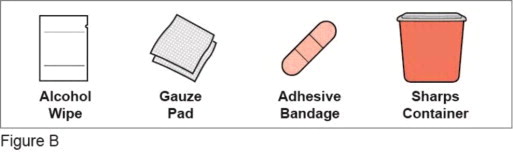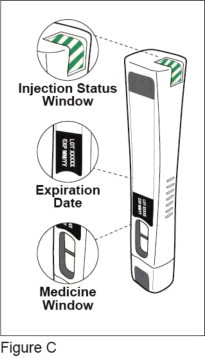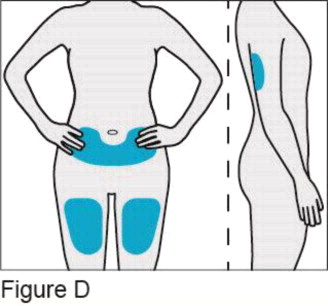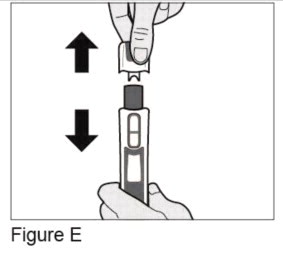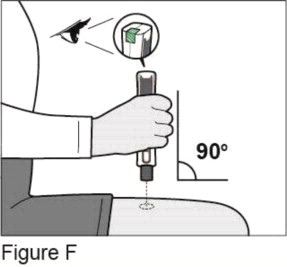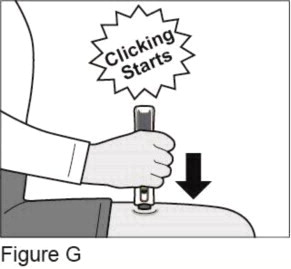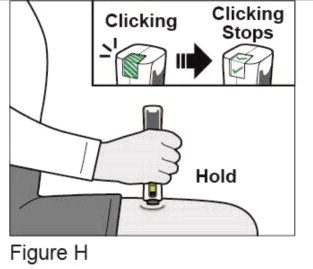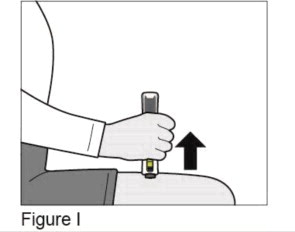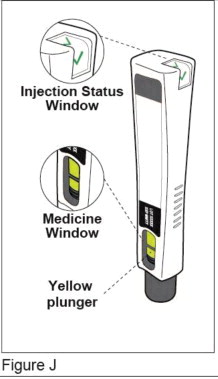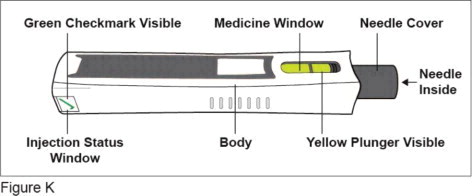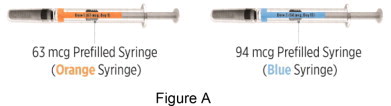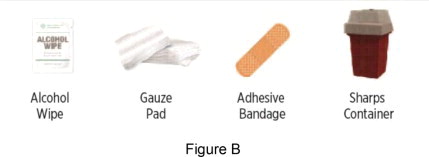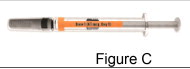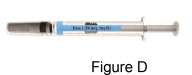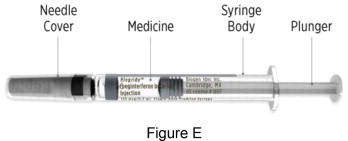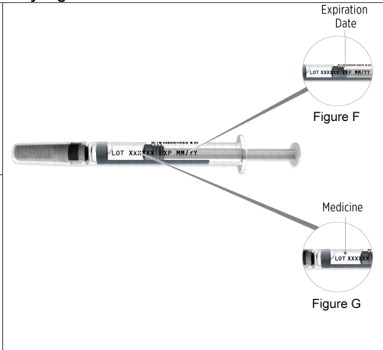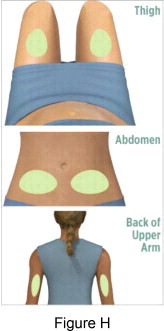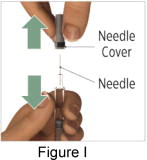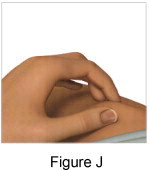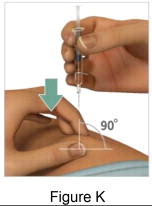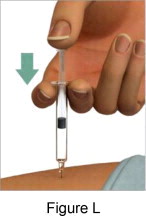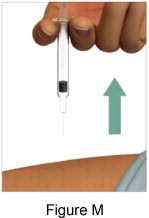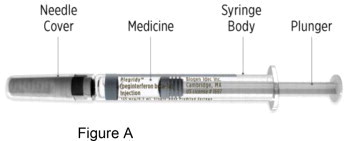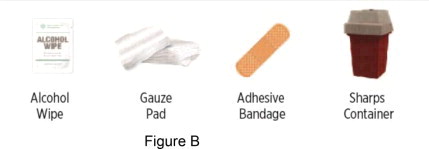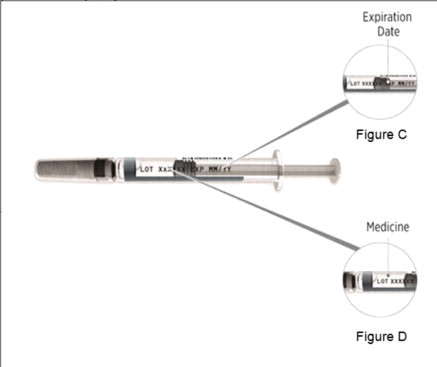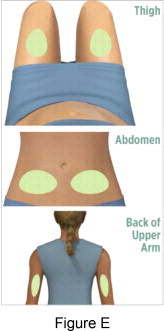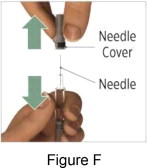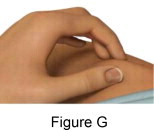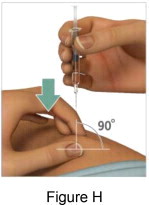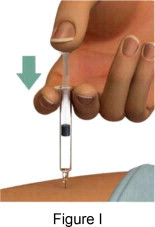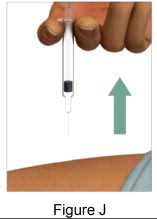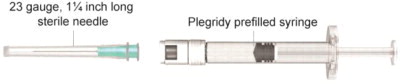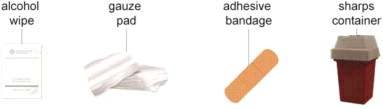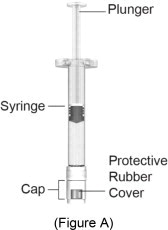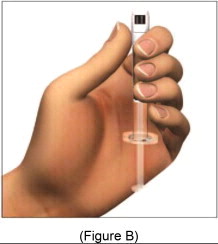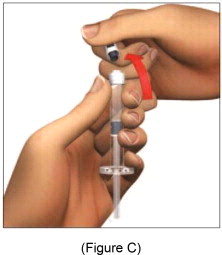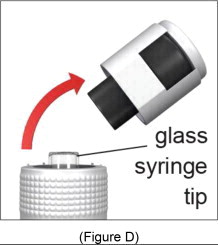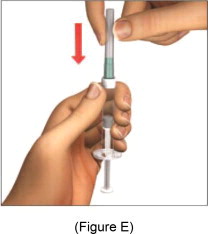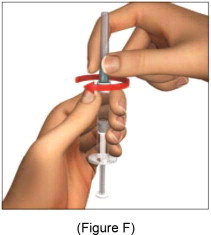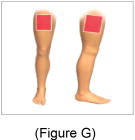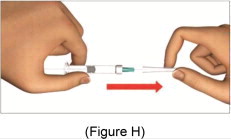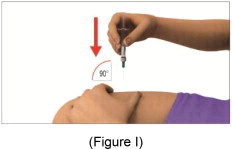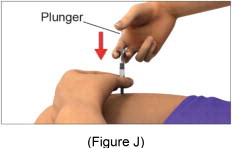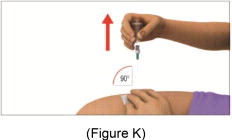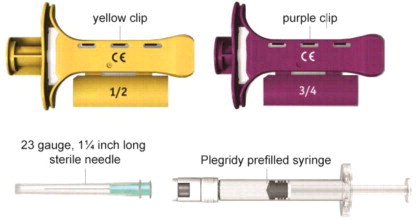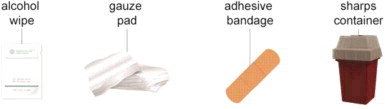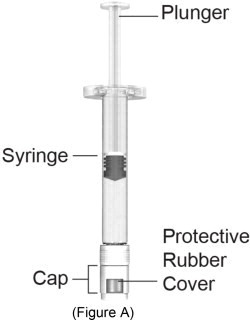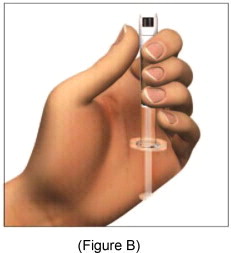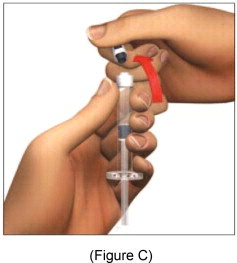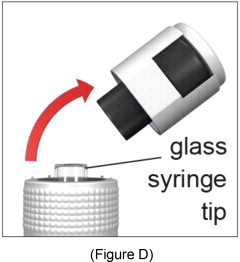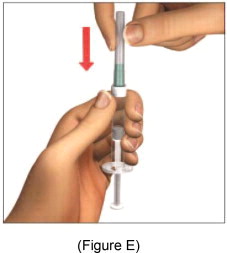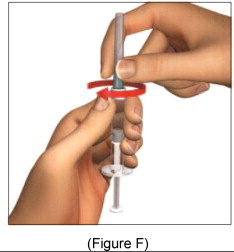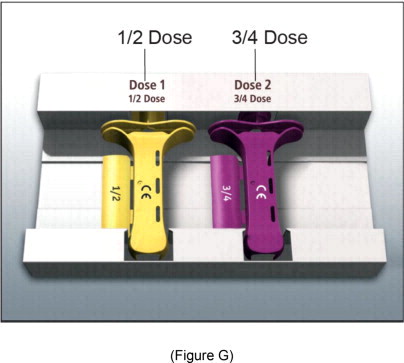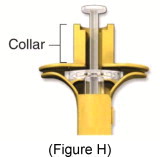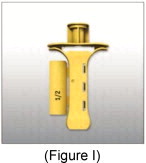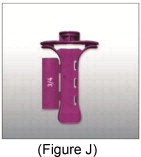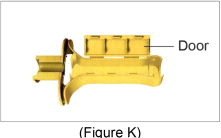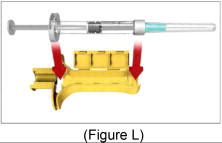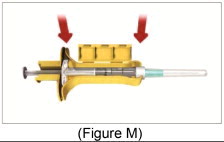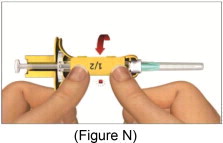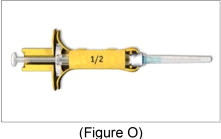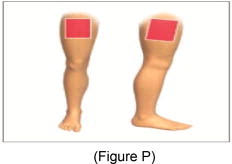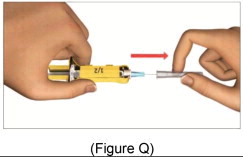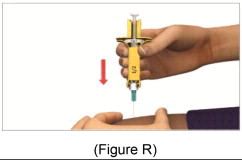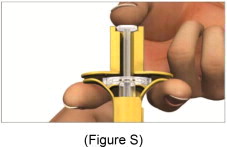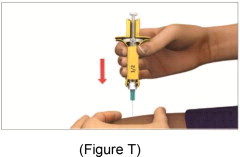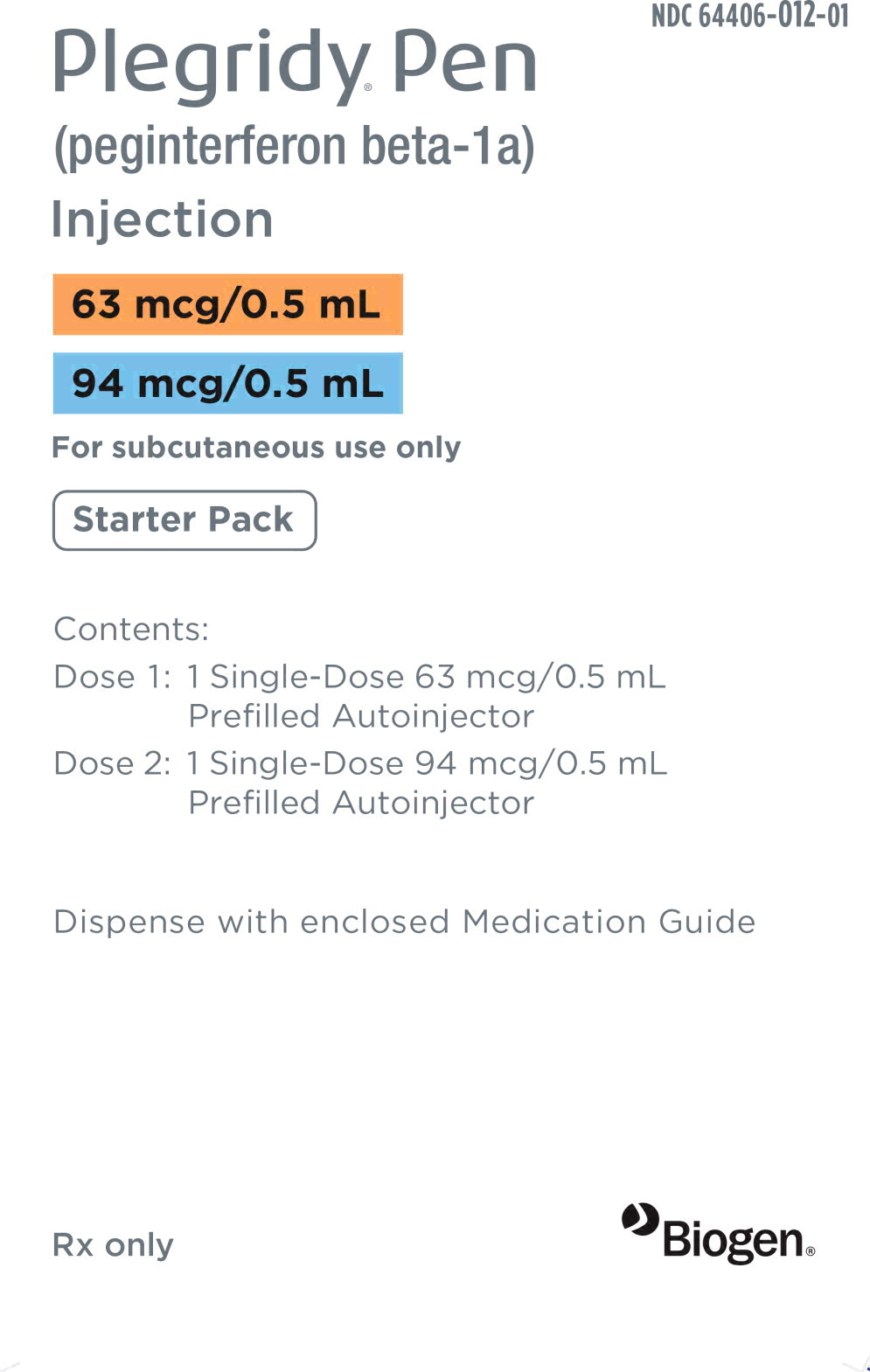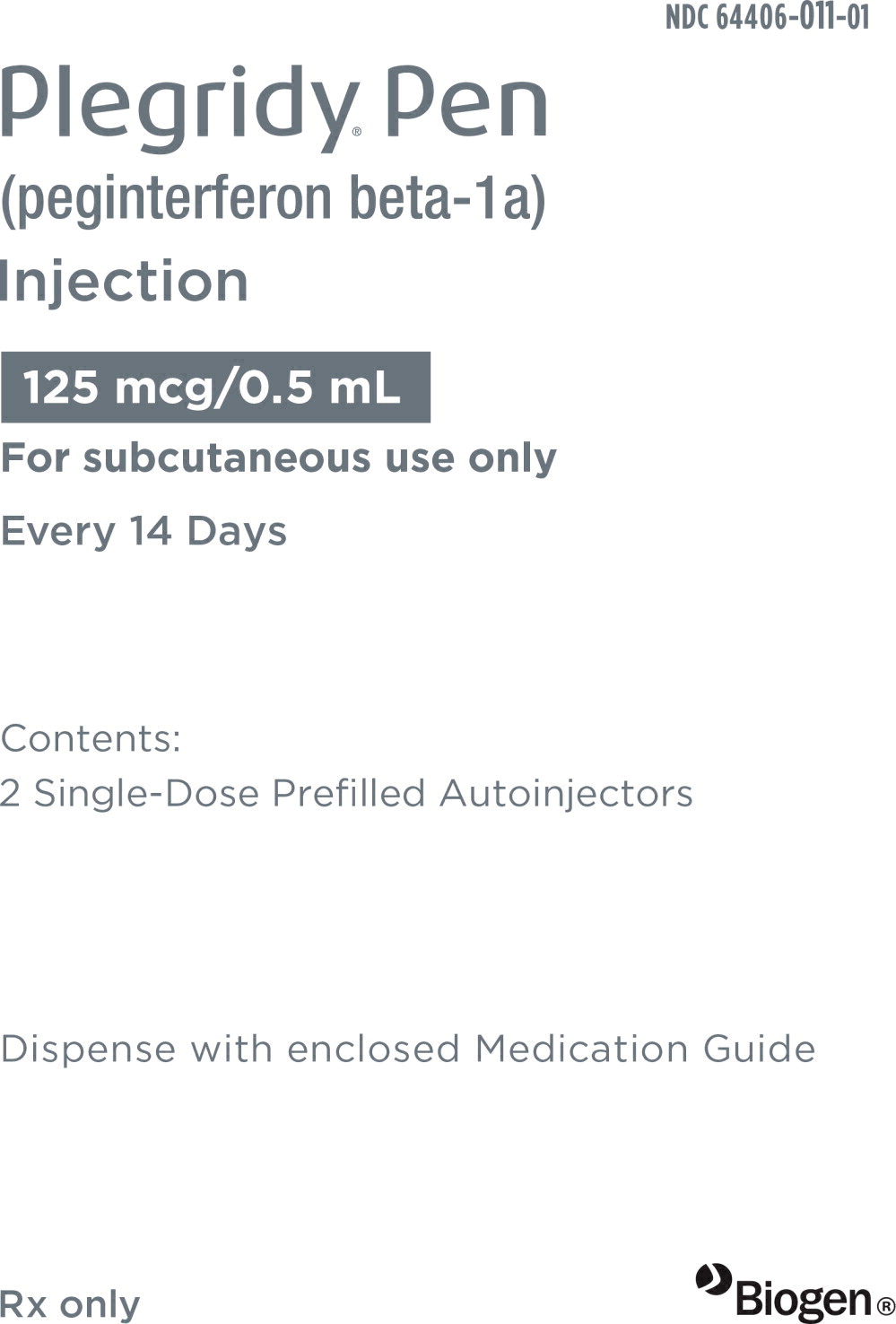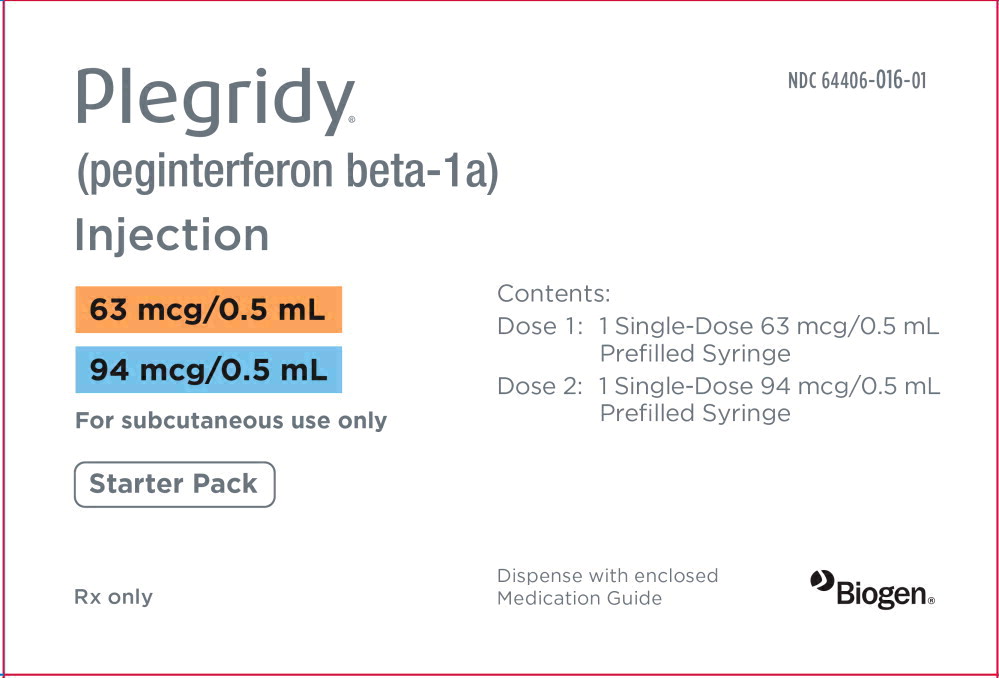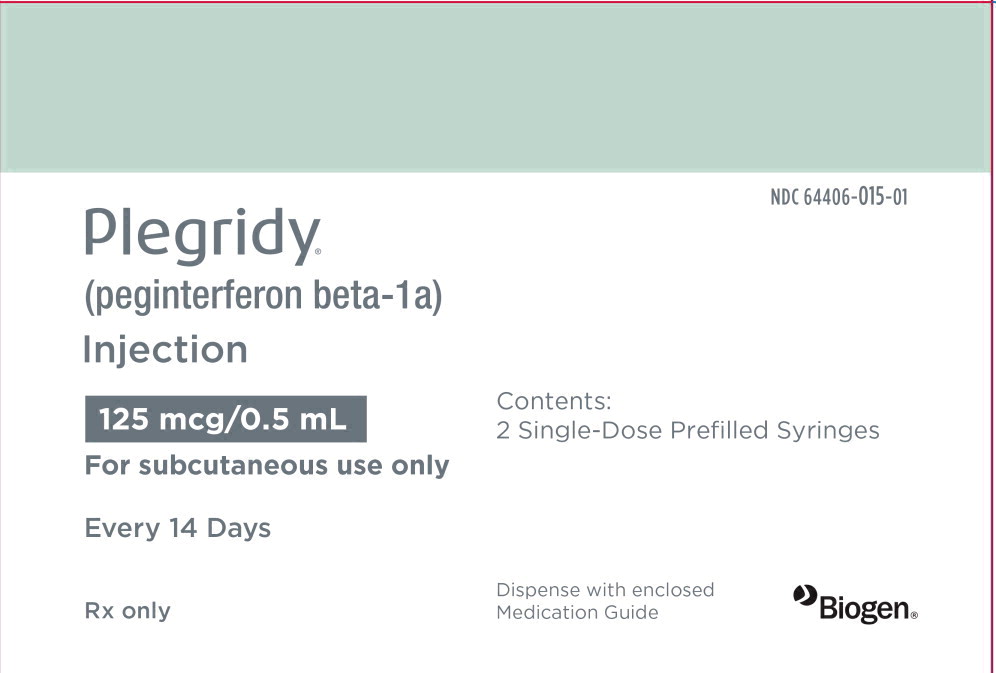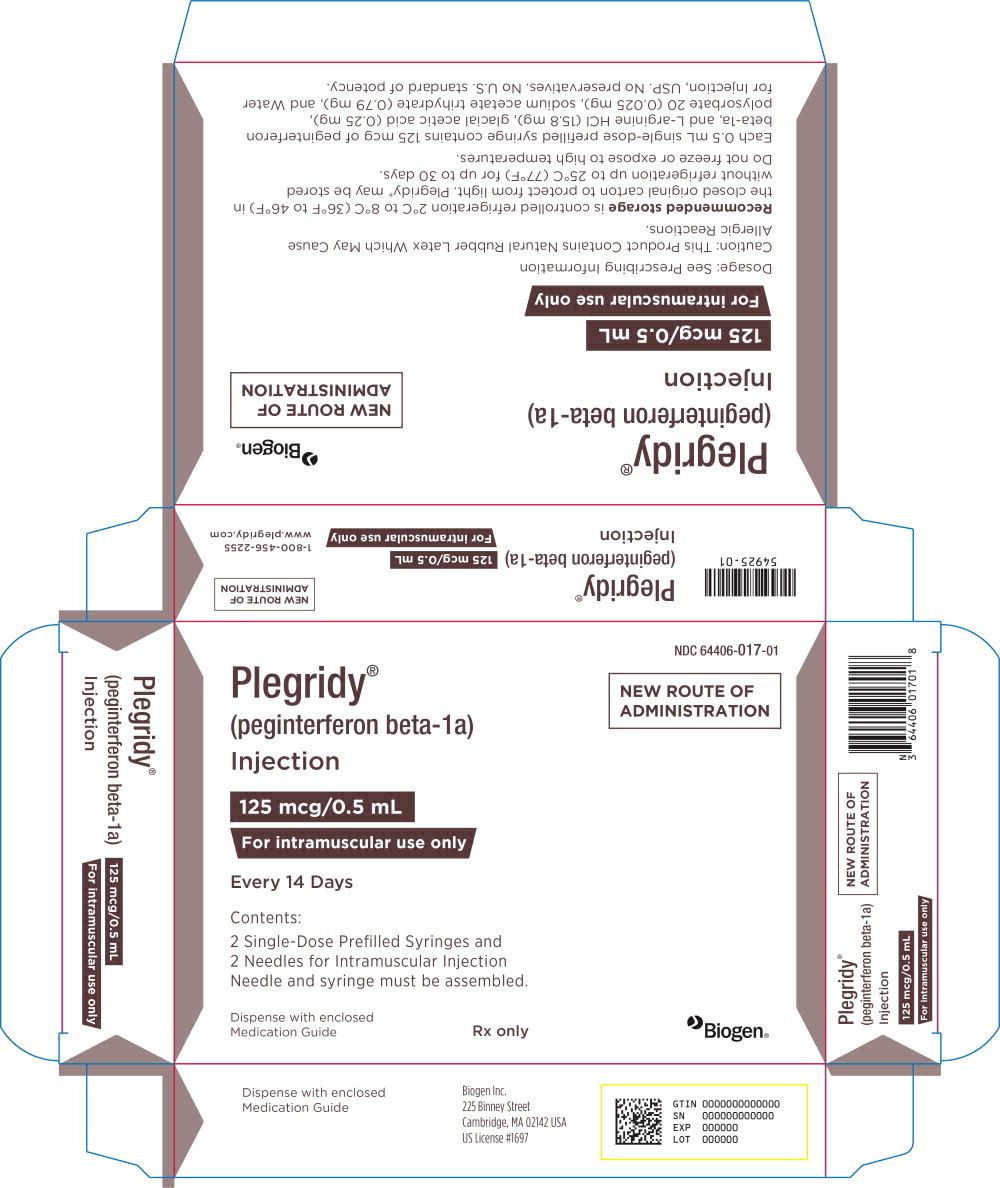 DRUG LABEL: Plegridy
NDC: 64406-015 | Form: INJECTION, SOLUTION
Manufacturer: Biogen Inc.
Category: prescription | Type: HUMAN PRESCRIPTION DRUG LABEL
Date: 20251021

ACTIVE INGREDIENTS: PEGINTERFERON BETA-1A 125 ug/0.5 mL
INACTIVE INGREDIENTS: ARGININE HYDROCHLORIDE 15.8 mg/0.5 mL; SODIUM ACETATE 0.79 mg/0.5 mL; ACETIC ACID 0.25 mg/0.5 mL; POLYSORBATE 20 0.025 mg/0.5 mL; WATER

HIGHLIGHTS OF PRESCRIBING INFORMATION

These highlights do not include all the information needed to use PLEGRIDY® safely and effectively. See full prescribing information for PLEGRIDY.
PLEGRIDY (peginterferon beta-1a) injection, for subcutaneous or intramuscular use
Initial U.S. Approval: 2014

RECENT MAJOR CHANGES

Warnings and Precautions (5.8) | 7/2023

1 INDICATIONS AND USAGE

PLEGRIDY is an interferon beta indicated for the treatment of relapsing forms of multiple sclerosis (MS), to include clinically isolated syndrome, relapsing-remitting disease, and active secondary progressive disease, in adults (1)

2 DOSAGE AND ADMINISTRATION

- For subcutaneous or intramuscular use only (2.1)
- Recommended dose: 125 micrograms every 14 days (2.1)
- PLEGRIDY dose should be titrated, starting with 63 micrograms on day 1, 94 micrograms on day 15, and 125 micrograms (full dose) on day 29 (2.1)
- A healthcare professional should train patients in the proper technique for self-administering subcutaneous injections using the prefilled pen or syringe or intramuscular injections using the prefilled syringe (2.2)
- Analgesics and/or antipyretics on treatment days may help ameliorate flu-like symptoms (2.3)

3 DOSAGE FORMS AND STRENGTHS

Subcutaneous Administration:

- Injection: 125 mcg/0.5 mL in a single-dose prefilled pen or single-dose prefilled syringe (3)
- Injection: 63 mcg/0.5 mL in a single-dose prefilled pen or single-dose prefilled syringe (3)
- Injection: 94 mcg/0.5 mL in a single-dose prefilled pen or single-dose prefilled syringe (3)

Intramuscular Administration:

- Injection: 125 mcg/0.5 mL solution in a single-dose prefilled syringe (3)

4 CONTRAINDICATIONS

History of hypersensitivity to natural or recombinant interferon beta or peginterferon, or any other component of PLEGRIDY (4)

5 WARNINGS AND PRECAUTIONS

- Hepatic injury: monitor liver function tests; monitor patients for signs and symptoms of hepatic injury; consider discontinuation of PLEGRIDY if hepatic injury occurs (5.1)
- Depression and suicide: advise patients to report immediately any symptom of depression or suicidal ideation to their healthcare provider; consider discontinuation of PLEGRIDY if depression occurs (5.2)
- Anaphylaxis and other allergic reactions: Discontinue PLEGRIDY if a serious allergic reaction occurs (5.3)
- Injection site reactions: Do not administer PLEGRIDY into affected area until fully healed; if multiple lesions occur, change injection site or discontinue PLEGRIDY until healing of skin lesions (5.4)
- Congestive heart failure: monitor patients with pre-existing significant cardiac disease for worsening of cardiac symptoms (5.5)
- Decreased peripheral blood counts: monitor complete blood counts (5.6)
- Thrombotic Microangiopathy: Cases of thrombotic microangiopathy have been reported with interferon beta products. Discontinue PLEGRIDY if clinical symptoms and laboratory findings consistent with TMA occur (5.7)
- Pulmonary Arterial Hypertension: Cases of pulmonary arterial hypertension (PAH) have been reported in patients treated with interferon beta products, including PLEGRIDY. Discontinue PLEGRIDY if PAH is diagnosed (5.8)
- Autoimmune disorders: consider discontinuation of PLEGRIDY if a new autoimmune disorder occurs (5.9)

6 ADVERSE REACTIONS

The most common adverse reactions in clinical trials of subcutaneous PLEGRIDY (incidence ≥10% and at least 2% more frequent on PLEGRIDY than on placebo) were injection site erythema, influenza-like illness, pyrexia, headache, myalgia, chills, injection site pain, asthenia, injection site pruritus, and arthralgia (6.1)

To report SUSPECTED ADVERSE REACTIONS, contact Biogen at 1-800-456-2255 or FDA at 1-800-FDA-1088 or http://www.fda.gov/medwatch.

8 USE IN SPECIFIC POPULATIONS

- Pregnancy: Epidemiological data do not suggest a clear relationship between interferon beta use and major congenital malformations, but interferon beta may cause fetal harm based on animal data (8.1)
- Severe Renal Impairment: monitor for adverse reactions (8.6)

FULL PRESCRIBING INFORMATION

1 INDICATIONS AND USAGE

PLEGRIDY is indicated for the treatment of relapsing forms of multiple sclerosis (MS), to include clinically isolated syndrome, relapsing-remitting disease, and active secondary progressive disease, in adults.

2 DOSAGE AND ADMINISTRATION

2.1 Dosing Information

PLEGRIDY may only be administered subcutaneously (SC) or intramuscularly (IM).

Recommended Maintenance Dosage

After initial titration (see Table 1 and Table 2), the recommended dosage of PLEGRIDY is 125 micrograms injected every 14 days.

For subcutaneous injection:

Patients may rotate injection sites between the abdomen, back of the upper arm, or thigh.

For intramuscular injection:

Patients may rotate injection sites between the left and right thighs.

Treatment Initiation

Dose titration at the initiation of treatment may help to ameliorate flu-like symptoms that can occur at treatment initiation with interferons. Prophylactic and concurrent use of analgesics and/or antipyretics may prevent or ameliorate flu-like symptoms sometimes experienced during treatment with PLEGRIDY.

Switching between the subcutaneous and intramuscular routes of administration and vice versa has not been studied. It is not expected that dose titration should be repeated to ameliorate flu-like symptoms if switching between subcutaneous and intramuscular routes of administration, or vice versa based upon bioequivalence demonstrated between the two routes of administration.

Subcutaneous Administration of PLEGRIDY

Patients using PLEGRIDY for the first time should start treatment with 63 micrograms on day 1. On day 15 (14 days later), the dose is increased to 94 micrograms, reaching the full dose of 125 micrograms on day 29 (after another 14 days). Patients continue with the full dose (125 micrograms) every 14 days thereafter (see Table 1). A PLEGRIDY Starter Pack is available containing two prefilled pens or syringes: 63 micrograms (dose 1) and 94 micrograms (dose 2).

Table 1: Schedule for Subcutaneous Dose Titration
Dose | Timea | Amount (micrograms) | Color of Pen or Syringe Label
Dose 1 | On day 1 | 63 | Orange
Dose 2 | On day 15 | 94 | Blue
Dose 3 | On day 29 and every 14 days thereafter | 125 (full dose) | Grey
a Dosed every 14 days

Intramuscular Administration of PLEGRIDY

For patients using PLEGRIDY injected intramuscularly for the first time, PLEGRIDY should be titrated using the PLEGRIDY Titration Kit designed for use with the prefilled syringe. The PLEGRIDY Titration Kit is supplied separately and contains two titration devices to be used only with PLEGRIDY prefilled syringes for intramuscular use.

Patients should start treatment with 63 micrograms (yellow clip) on day 1. On day 15 (14 days later), the dose is increased to 94 micrograms (purple clip), reaching the full dose of 125 micrograms on day 29 (after another 14 days). Patients continue with the full dose (125 micrograms) every 14 days thereafter (see Table 2).

Table 2: Schedule for Intramuscular Dose Titration
Dose | Timea | Amount (micrograms) | Titration Clip
Dose 1 | On day 1 | 63 | Yellow
Dose 2 | On day 15 | 94 | Purple
Dose 3 | On day 29 and every 14 days thereafter | 125 (full dose) | No Clips Needed
a Dosed every 14 days

2.2 Important Administration Instructions (All Dosage Forms)

Healthcare professionals should train patients in the proper technique for self-administering subcutaneous injections using the prefilled pen or syringe or intramuscular injections using the prefilled syringe. Parenteral drug products should be inspected visually for particulate matter and discoloration prior to administration. Advise patients and caregivers to rotate injection sites with each administration to minimize the likelihood of severe injection site reactions, including necrosis or localized infection [see Warnings and Precautions (5.4)].

Once removed from the refrigerator, PLEGRIDY should be allowed to warm to room temperature (about 30 minutes) prior to injection. Do not use external heat sources such as hot water to warm PLEGRIDY.

Each PLEGRIDY pen and syringe for subcutaneous injection is provided with the needle pre-attached. PLEGRIDY prefilled syringe for intramuscular injection is supplied as a prefilled syringe with a separate needle. Both intramuscular and subcutaneous prefilled syringes and subcutaneously administered prefilled pens are for one-time use in one patient only and should be discarded after use.

2.3 Premedication for Flu-like Symptoms

Prophylactic and concurrent use of analgesics and/or antipyretics may prevent or ameliorate flu-like symptoms sometimes experienced during treatment with PLEGRIDY.

3 DOSAGE FORMS AND STRENGTHS

PLEGRIDY is a clear to slightly opalescent and colorless to slightly yellow solution.

Subcutaneous Administration:

- Injection: 125 mcg/0.5 mL in a single-dose prefilled pen or single-dose prefilled syringe
- Injection: 63 mcg/0.5 mL in a single-dose prefilled pen or a single-dose prefilled syringe
- Injection: 94 mcg/0.5 mL in a single-dose prefilled pen or a single-dose prefilled syringe

Intramuscular Administration:

- Injection: 125 mcg/0.5 mL in a single-dose prefilled syringe

4 CONTRAINDICATIONS

PLEGRIDY is contraindicated in patients with a history of hypersensitivity to natural or recombinant interferon beta or peginterferon, or any other component of PLEGRIDY [see Warnings and Precautions (5.3)].

5 WARNINGS AND PRECAUTIONS

5.1 Hepatic Injury

Severe hepatic injury, including hepatitis, autoimmune hepatitis, and rare cases of severe hepatic failure, have been reported with interferon beta. Asymptomatic elevation of hepatic transaminases has also been reported, and in some patients has recurred upon rechallenge with interferon beta.

Elevations in hepatic enzymes and hepatic injury have been observed with the use of PLEGRIDY in clinical studies. The incidence of increases in hepatic transaminases was greater in patients taking PLEGRIDY than in those taking placebo. The incidence of elevations of alanine aminotransferase above 5 times the upper limit of normal was 1% in placebo-treated patients and 2% in PLEGRIDY-treated patients. The incidence of elevations of aspartate aminotransferase above 5 times the upper limit of normal was less than 1% in placebo-treated patients and less than 1% in PLEGRIDY-treated patients. Elevations of serum hepatic transaminases combined with elevated bilirubin occurred in 2 patients. Both cases resolved following discontinuation of PLEGRIDY.

Cases of noninfectious hepatitis have been reported in the postmarketing setting with use of PLEGRIDY.

Monitor patients for signs and symptoms of hepatic injury.

5.2 Depression and Suicide

Depression, suicidal ideation, and suicide occur more frequently in patients receiving interferon beta than in patients receiving placebo.

In clinical studies, the overall incidence of adverse events related to depression and suicidal ideation in multiple sclerosis patients was 8% in both the PLEGRIDY and placebo groups. The incidence of serious events related to depression and suicidal ideation was similar and less than 1% in both groups.

Advise patients to report immediately any symptom of depression or suicidal ideation to their healthcare provider. If a patient develops depression or other severe psychiatric symptoms, consider stopping treatment with PLEGRIDY.

5.3 Anaphylaxis and Other Allergic Reactions

Serious allergic reactions are rare complications of treatment with interferon beta; anaphylaxis has been reported with use of PLEGRIDY in the postmarketing setting.

Less than 1% of PLEGRIDY-treated patients experienced a serious allergic reaction such as angioedema or urticaria. Those who did have serious allergic reactions recovered promptly after treatment with antihistamines or corticosteroids. Discontinue PLEGRIDY if a serious allergic reaction occurs.

The protective rubber cover of the PLEGRIDY prefilled syringe for intramuscular administration contains natural rubber latex which may cause allergic reactions and should not be handled by latex-sensitive individuals. The safe use of PLEGRIDY prefilled syringe in latex-sensitive individuals has not been studied.

5.4 Injection Site Reactions Including Necrosis

Injection site reactions, including injection site necrosis, can occur with the use of interferon beta, including PLEGRIDY.

In clinical studies of subcutaneous PLEGRIDY, the incidence of injection site reactions (e.g., injection site erythema, pain, pruritus, or edema) was 66% in the PLEGRIDY group and 11% in the placebo group; the incidence of severe injection site reactions was 3% in the PLEGRIDY group and 0% in the placebo group. One patient out of 1468 patients who received PLEGRIDY in clinical studies experienced injection site necrosis. The injury resolved with standard medical treatment.

In Study 3, which compared single doses of intramuscular and subcutaneous PLEGRIDY [see Adverse Reactions (6.1)], the incidence of injection site reactions (e.g., injection site erythema, pain, pruritus, or edema) was 14% in the intramuscular PLEGRIDY group and 32% in the subcutaneous PLEGRIDY group.

Injection site abscesses and cellulitis have been reported in the postmarketing setting with use of interferon beta. Some cases required treatment with hospitalization for surgical drainage and intravenous antibiotics.

Periodically evaluate patient understanding and use of aseptic self-injection techniques and procedures, particularly if injection site necrosis has occurred.

Decisions to discontinue therapy following necrosis at a single injection site should be based on the extent of the necrosis. For patients who continue therapy with PLEGRIDY after injection site necrosis has occurred, avoid administration of PLEGRIDY near the affected area until it is fully healed. If multiple lesions occur, change injection site or discontinue PLEGRIDY until healing occurs.

5.5 Congestive Heart Failure

Congestive heart failure, cardiomyopathy, and cardiomyopathy with congestive heart failure occur in patients receiving interferon beta.

In clinical studies, the incidence of cardiovascular events was 7% in both PLEGRIDY and placebo treatment groups. No serious cardiovascular events were reported in the PLEGRIDY group.

Monitor patients with significant cardiac disease for worsening of their cardiac condition during initiation and continuation of treatment with PLEGRIDY.

5.6 Decreased Peripheral Blood Counts

Interferon beta can cause decreased peripheral blood counts in all cell lines, including rare instances of pancytopenia and severe thrombocytopenia.

In clinical studies, decreases in white blood cell counts below 3.0 x 10^9/L occurred in 7% of patients receiving PLEGRIDY and in 1% receiving placebo. There is no apparent association between decreases in white blood cell counts and an increased risk of infections or serious infections. The incidence of clinically significant decreases in lymphocyte counts (below 0.5 x 10^9/L), neutrophil counts (below 1.0 x 10^9/L), and platelet counts (below 100 x 10^9/L) were all less than 1% and similar in both placebo and PLEGRIDY groups. Two serious cases were reported in patients treated with PLEGRIDY: one patient (less than 1%) experienced severe thrombocytopenia (defined as a platelet count less than or equal to 10 x 10^9/L), and another patient (less than 1%) experienced severe neutropenia (defined as a neutrophil count less than or equal to 0.5 x 10^9/L). In both patients, cell counts recovered after discontinuation of PLEGRIDY. Compared to placebo, there were no significant differences in red blood cell counts in patients treated with PLEGRIDY.

Monitor patients for infections, bleeding, and symptoms of anemia. Monitor complete blood cell counts, differential white blood cell counts, and platelet counts during treatment with PLEGRIDY. Patients with myelosuppression may require more intensive monitoring of blood cell counts.

5.7 Thrombotic Microangiopathy

Cases of thrombotic microangiopathy (TMA), including thrombotic thrombocytopenic purpura and hemolytic uremic syndrome, some fatal, have been reported with interferon beta products. Cases have been reported several weeks to years after starting interferon beta products. Discontinue PLEGRIDY if clinical symptoms and laboratory findings consistent with TMA occur, and manage as clinically indicated.

5.8 Pulmonary Arterial Hypertension

Cases of pulmonary arterial hypertension (PAH) have been reported in patients treated with interferon beta products, including PLEGRIDY. PAH has occurred in patients treated with interferon beta products in the absence of other contributory factors. Many of the reported cases required hospitalization, including one case with interferon beta in which the patient underwent a lung transplant. PAH has developed at various time points after initiating therapy with interferon beta products and may occur several years after starting treatment.

Patients who develop unexplained symptoms (e.g., dyspnea, new or increasing fatigue) should be assessed for PAH. If alternative etiologies have been ruled out and a diagnosis of PAH is confirmed, discontinue treatment and manage as clinically indicated.

5.9 Autoimmune Disorders

Autoimmune disorders of multiple target organs including idiopathic thrombocytopenia, hyper- and hypothyroidism, and autoimmune hepatitis have been reported with interferon beta.

In clinical studies, the incidence of autoimmune disorders was less than 1% in both PLEGRIDY and placebo treatment groups.

If patients develop a new autoimmune disorder, consider stopping PLEGRIDY.

5.10 Seizures

Seizures are associated with the use of interferon beta.

The incidence of seizures in multiple sclerosis clinical studies was less than 1% in patients receiving PLEGRIDY and placebo.

Exercise caution when administering PLEGRIDY to patients with a seizure disorder.

6 ADVERSE REACTIONS

The following serious adverse reactions are discussed in more detail in other sections of labeling:

- Hepatic Injury [see Warnings and Precautions (5.1)]
- Depression and Suicide [see Warnings and Precautions (5.2)]
- Anaphylaxis and Other Allergic Reactions [see Warnings and Precautions (5.3)]
- Injection Site Reactions Including Necrosis [see Warnings and Precautions (5.4)]
- Congestive Heart Failure [see Warnings and Precautions (Section 5.5)]
- Decreased Peripheral Blood Counts [see Warnings and Precautions (5.6)]
- Thrombotic Microangiopathy [see Warnings and Precautions (5.7)]
- Pulmonary Arterial Hypertension [see Warnings and Precautions (5.8)]
- Autoimmune Disorders [see Warnings and Precautions (5.9)]
- Seizures [see Warnings and Precautions (5.10)]

6.1 Clinical Trials Experience

Because clinical trials are conducted under widely varying conditions, adverse reaction rates observed in the clinical trials of PLEGRIDY cannot be directly compared to rates in clinical trials of other drugs and may not reflect the rates observed in practice.

PLEGRIDY Via Subcutaneous Administration

In clinical studies (Study 1 and Study 2), a total of 1468 patients with relapsing multiple sclerosis received PLEGRIDY by subcutaneous injection for up to 177 weeks (41 months), with an overall exposure equivalent to 1932 person-years. A total of 1093 patients received at least 1 year, and 415 patients at least 2 years of treatment with PLEGRIDY. A total of 512 and 500 patients, respectively, received PLEGRIDY 125 micrograms every 14 days or every 28 days during the placebo-controlled phase of Study 1 (year 1). The experience in year 2 of Study 1 and in the 2-year safety extension study (Study 2) was consistent with the experience in the 1-year placebo-controlled phase of Study 1.

In the placebo-controlled phase of Study 1, the most common adverse drug reactions for PLEGRIDY 125 micrograms subcutaneously every 14 days were injection site erythema, influenza-like illness, pyrexia, headache, myalgia, chills, injection site pain, asthenia, injection site pruritus, and arthralgia (all had incidence more than 10% and at least 2% more than placebo). The most commonly reported adverse event leading to discontinuation in patients treated with PLEGRIDY 125 micrograms subcutaneously every 14 days was influenza-like illness (in less than 1% of patients).

Table 3 summarizes adverse reactions reported over 48 weeks from patients treated in the placebo-controlled phase of Study 1 who received subcutaneous PLEGRIDY 125 micrograms (n=512), or placebo (n=500), every 14 days.

Table 3: Adverse Reactions in the 48-Week Placebo-Controlled Phase of Study 1 with an Incidence 2% Higher for PLEGRIDY Than for Placebo
 | PLEGRIDY (N=512) % | Placebo (N=500) %
Nervous System Disorders
Headache | 44 | 33
Gastrointestinal Disorders
Nausea | 9 | 6
Vomiting | 5 | 2
Musculoskeletal and Connective Tissue Disorders
Myalgia | 19 | 6
Arthralgia | 11 | 7
General Disorders and Administration Site Conditions
Injection site erythema | 62 | 7
Influenza like illness | 47 | 13
Pyrexia | 45 | 15
Chills | 17 | 5
Injection site pain | 15 | 3
Asthenia | 13 | 8
Injection site pruritus | 13 | 1
Hyperthermia | 4 | 1
Pain | 5 | 3
Injection site edema | 3 | 0
Injection site warmth | 3 | 0
Injection site hematoma | 3 | 1
Injection site rash | 2 | 0
Investigations
Body temperature increased | 6 | 3
Alanine aminotransferase increased | 6 | 3
Aspartate aminotransferase increased | 4 | 2
Gamma-glutamyl-transferase increased | 3 | 1
Skin and Subcutaneous Tissue Disorder
Pruritus | 4 | 1

Flu-Like Symptoms

Influenza-like illness was experienced by 47% of patients receiving PLEGRIDY 125 micrograms every 14 days and 13% of patients receiving placebo. Fewer than 1% of PLEGRIDY-treated patients in Study 1 discontinued treatment due to flu-like symptoms.

Comparison Between Subcutaneous and Intramuscular Administration

An open-label, crossover study analyzed findings from 130 healthy volunteers to assess the bioequivalence of single doses of 125 micrograms of PLEGRIDY administered as a subcutaneous and intramuscular injection (Study 3).

The most commonly reported adverse reactions (with >10% incidence in either arm) across both treatment periods were chills (36% in IM vs 27% in SC), pain (22% in IM vs 14% in SC), headache (36% in IM vs 41% in SC), injection site pain (11% in IM vs 15% in SC), and injection site erythema (2% in IM vs 25% in SC). Overall, injection site reactions were reported in 14% via IM route as compared to 32% via SC route.

6.2 Immunogenicity

As with all therapeutic proteins, there is a potential for immunogenicity.

The detection of antibody formation is highly dependent on the sensitivity and specificity of the assay. Additionally, the observed incidence of antibody (including neutralizing antibody) positivity in an assay may be influenced by several factors including assay methodology, sample handling, timing of sample collection, concomitant medications, and underlying disease. For these reasons, comparison of the incidence of antibodies in the studies described below with the incidence of antibodies in other studies or to other interferon beta-1a products may be misleading.

In Study 1, fewer than 1% of patients treated with PLEGRIDY SC every 14 days for 1 year developed neutralizing antibodies. Approximately 7% of PLEGRIDY SC-treated patients developed antibodies to the polyethylene glycol moiety.

No formal studies have been conducted with regards to immunogenicity of the intramuscular route of administration of PLEGRIDY.

6.3 Postmarketing Experience

The following adverse reactions have been identified during post-approval use of PLEGRIDY. Because these reactions are reported voluntarily from a population of uncertain size, it is not always possible to reliably estimate their frequency or establish a causal relationship to drug exposure.

Anaphylactic reactions

In post marketing experience, serious hypersensitivity reactions, including cases of anaphylaxis, have been reported following PLEGRIDY administration [see Warnings and Precautions (5.3)].

Hepatic injury

In post marketing experience, noninfectious hepatitis (including serious hepatitis) cases have been reported following PLEGRIDY administration [see Warnings and Precautions (5.1)].

Pulmonary Arterial Hypertension

In postmarketing experience, pulmonary arterial hypertension has been reported following PLEGRIDY administration [see Warnings and Precautions (5.8)].

8 USE IN SPECIFIC POPULATIONS

8.1 Pregnancy

Risk Summary

Data from a large population-based cohort study, as well as other published studies over several decades, have not identified a drug-associated risk of major birth defects with the use of interferon beta products during early pregnancy. Findings regarding a potential risk for low birth weight or miscarriage with the use of interferon beta products in pregnancy have been inconsistent (see Data). In a study in pregnant monkeys, administration of interferon beta during pregnancy resulted in an increased rate of abortion (see Data).

In the U.S. general population, the estimated background risk of major birth defects and miscarriage in clinically recognized pregnancies is 2-4% and 15-20%, respectively. The background risk of major birth defects and miscarriage for the indicated population is unknown.

Data

Human Data

The majority of observational studies reporting on pregnancies exposed to interferon beta products did not identify an association between the use of interferon beta products during early pregnancy and an increased risk of major birth defects.

In a population-based cohort study conducted in Finland and Sweden, data were collected from 1996--2014 in Finland and 2005--2014 in Sweden on 2,831 pregnancy outcomes from women with MS. 797 pregnancies were in women exposed to interferon beta only. No evidence was found of an increased risk of major birth defects among women with MS exposed to interferon beta products compared to women with MS that were unexposed to any non-steroid therapy for MS (n=1,647) within the study. No increased risks were observed for miscarriages and ectopic pregnancies, though there were limitations in obtaining complete data capture for these outcomes, making the interpretation of the findings more difficult.

Two small cohort studies that examined pregnancies exposed to interferon beta products (without differentiating between subtypes of interferon beta products) suggested that a decrease in mean birth weight may be associated with interferon beta exposure during pregnancy, but this finding was not confirmed in larger observational studies. Two small studies observed an increased prevalence of miscarriage, although the finding was only statistically significant in one study. Most studies enrolled patients later in pregnancy, which made it difficult to ascertain the true percentage of miscarriages. In one small cohort study, a significantly increased risk of preterm birth following interferon beta exposure during pregnancy was observed.

Animal Data

PLEGRIDY has not been tested for developmental toxicity in pregnant animals. In monkeys given interferon beta by subcutaneous injection every other day during early pregnancy, no adverse effects on embryofetal development were observed. Abortifacient activity was evident following 3 to 5 doses.

8.2 Lactation

Risk Summary

Limited published literature has described the presence of interferon beta-1a products in human milk at low levels. There are no data on the effects of interferon beta-1a on milk production. Therefore, the developmental and health benefits of breastfeeding should be considered along with the mother's clinical need for PLEGRIDY and any potential adverse effects on the breastfed infant from PLEGRIDY or from the underlying maternal condition.

8.4 Pediatric Use

Safety and effectiveness in pediatric patients have not been established.

8.5 Geriatric Use

Clinical studies of PLEGRIDY did not include sufficient numbers of subjects aged 65 and over to determine whether they respond differently from younger subjects. Other reported clinical experience has not identified differences in responses between the elderly and younger patients.

8.6 Renal Impairment

Monitor for adverse reactions due to increased drug exposure in patients with severe renal impairment [see Clinical Pharmacology (12.3)].

11 DESCRIPTION

Peginterferon beta-1a is a covalent conjugate of recombinant interferon beta-1a (approximate molecular weight [MW] 20,000 daltons) with a single, linear methoxy poly(ethyleneglycol)-O-2-methylpropionaldehyde molecule (approximate MW 20,000 daltons). Interferon beta-1a is produced as a glycosylated protein using genetically-engineered Chinese hamster ovary cells into which the human interferon beta gene has been introduced. The amino acid sequence of recombinant interferon beta-1a is identical to that of the human interferon beta counterpart.

The molecular weight of peginterferon beta-1a is approximately 44,000 daltons, consistent with the mass of the protein, the carbohydrate moieties (approximately 2,500 daltons), and the attached poly(ethylene glycol).

Peginterferon beta-1a 125 mcg contains 125 mcg of interferon beta-1a plus 125 mcg of poly(ethylene glycol). Using the World Health Organization International Standard for interferon beta, peginterferon beta-1a has a specific antiviral activity of approximately 100 million International Units (MIU) per mg of protein as determined using an in vitro cytopathic effect assay. Peginterferon beta-1a 125 mcg contains approximately 12 MIU of antiviral activity.

Subcutaneous Administration

PLEGRIDY (peginterferon beta-1a) injection is a sterile, preservative-free solution in a single-dose prefilled pen or single-dose prefilled syringe with a 29-gauge, 0.5-inch needle for subcutaneous use. Each prefilled pen or prefilled syringe delivers 0.5 mL. Each 0.5 mL contains 63 mcg, 94 mcg, or 125 mcg of peginterferon beta-1a, and L-arginine HCl (15.8 mg), glacial acetic acid (0.25 mg), polysorbate 20 (0.025 mg), and sodium acetate trihydrate (0.79 mg) in Water for Injection, USP. The pH is approximately 4.8.

Intramuscular Administration

PLEGRIDY (peginterferon beta-1a) injection is a sterile, preservative-free solution in a single-dose prefilled syringe with a 23-gauge, 1.25-inch needle for intramuscular use. Each prefilled syringe delivers 0.5 mL. Each 0.5 mL contains 125 mcg of peginterferon beta-1a, and L-arginine HCl (15.8 mg), glacial acetic acid (0.25 mg), polysorbate 20 (0.025 mg), and sodium acetate trihydrate (0.79 mg) in Water for Injection, USP. The pH is approximately 4.8.

12 CLINICAL PHARMACOLOGY

12.1 Mechanism of Action

The mechanism by which PLEGRIDY exerts its effects in patients with multiple sclerosis is unknown.

12.2 Pharmacodynamics

There is no biochemical or physiologic effect known to relate directly to the clinical effect of PLEGRIDY.

12.3 Pharmacokinetics

After single-dose or multiple-dose subcutaneous administration of PLEGRIDY to healthy subjects, serum PLEGRIDY peak concentration (Cmax) and total exposure over time (area under the curve, or AUC) increased in proportion to doses from 63 to 188 micrograms. PLEGRIDY did not accumulate in the serum after multiple doses of 125 micrograms every 14 days. Pharmacokinetic parameters for PLEGRIDY, including Cmax and AUC, did not differ significantly between healthy volunteers and multiple sclerosis patients or between single-dose and multiple-dose administrations. However, the coefficient of variation between individual patients for AUC, Cmax, and half-life was high (41% to 68%, 74% to 89%, and 45% to 93%, respectively).

Absorption

After 125 microgram subcutaneous doses of PLEGRIDY in multiple sclerosis patients, the maximum concentration occurred between 1 and 1.5 days, the mean Cmax was 280 pg/mL, and the AUC over the 14 day dosing interval was 34.8 ng.hr/mL.

Distribution

In multiple sclerosis patients taking 125 microgram subcutaneous doses of PLEGRIDY every 14 days, the estimated volume of distribution was 481 liters.

Metabolism and Elimination

Clearance mechanisms for PLEGRIDY include catabolism and excretion. The major pathway of elimination is renal. The half-life is approximately 78 hours in multiple sclerosis patients. The mean steady state clearance of PLEGRIDY is approximately 4.1 L/hr. PLEGRIDY is not extensively metabolized in the liver.

The pharmacokinetics of 125 μg single dose of PLEGRIDY administered subcutaneously and intramuscularly were similar.

Specific Populations

Body weight, gender, and age do not require dosage adjustment.

Renal impairment can increase the Cmax and AUC for PLEGRIDY. Results of a pharmacokinetic study in patients with mild, moderate, and severe renal impairment (creatinine clearance 50 to 80, 30 to 50, and less than 30 mL/minute, respectively) showed increases above normal for Cmax of 27%, 26%, and 42%, and for AUC, increases of 30%, 40%, and 53%. The half-life was 53, 49, and 82 hours in patients with mild, moderate, and severe renal impairment, respectively, compared to 54 hours in normal subjects.

In the same study, subjects with end stage renal disease requiring hemodialysis two or three times weekly had AUC and Cmax of PLEGRIDY values that were similar to those of normal controls. Each hemodialysis session removed approximately 24% of circulating PLEGRIDY from the systemic circulation [see Use in Specific Populations (8.6)].

13 NONCLINICAL TOXICOLOGY

13.1 Carcinogenesis, Mutagenesis, Impairment of Fertility

Carcinogenesis

The carcinogenic potential of PLEGRIDY has not been tested in animals.

Mutagenesis

PLEGRIDY was not mutagenic when tested in an in vitro bacterial reverse mutation (Ames) test and was not clastogenic in an in vitro assay in human lymphocytes.

Impairment of Fertility

In monkeys administered interferon beta by subcutaneous injection over the course of one menstrual cycle, menstrual irregularities, anovulation, and decreased serum progesterone levels were observed. These effects were reversible after discontinuation of drug.

14 CLINICAL STUDIES

The efficacy of PLEGRIDY was demonstrated in the randomized, double-blind, and placebo-controlled phase (year 1) of Study 1. The trial compared clinical and MRI outcomes at 48 weeks in patients who received PLEGRIDY 125 micrograms (n=512) or placebo (n=500) by the subcutaneous route, once every 14 days.

Study 1 enrolled patients who had a baseline Expanded Disability Status Scale (EDSS) score from 0 to 5, who had experienced at least 2 relapses within the previous three years, and had experienced at least 1 relapse in the previous year. The trial excluded patients with progressive forms of multiple sclerosis. The mean age of the study population was 37 years, the mean disease duration was 3.6 years, and the mean EDSS score at baseline was 2.46. The majority of the patients were women (71%).

The trial scheduled neurological evaluations at baseline, every 12 weeks, and at the time of a suspected relapse. Brain MRI evaluations were scheduled at baseline, week 24, and week 48.

The primary outcome was the annualized relapse rate over 1 year. Secondary outcomes included the proportion of patients relapsing, number of new or newly enlarging T2 hyperintense lesions, and time to confirmed disability progression. Confirmed disability progression was defined as follows: if the baseline EDSS score was 0, a sustained 12-week increase in EDSS score of 1.5 points was required; if the baseline EDSS score was greater than 0, a sustained 12-week increase in EDSS score of 1 point was required. Table 4 and Figure 1 show the results of Study 1.

Table 4: Clinical and MRI Results of Study 1
Endpoint | PLEGRIDY 125 micrograms every 14 days | Placebo | p-value
Clinical outcomes at 48 weeks | N=512 | N=500
Annualized relapse rate | 0.26 | 0.40 | 0.0007
Relative reduction | 36%
Proportion of patients with relapses | 0.19 | 0.29 | 0.0003
Relative risk reduction | 39%
Proportion of patients with disability progression | 0.07 | 0.11 | 0.0383
Relative risk reduction | 38%
MRI outcomes at 48 weeks | N=457 | N=476
Mean number of new or newly enlarging T2 hyperintense lesions | 3.6 | 10.9 | <0.0001
Relative reduction | 67%
Mean number of Gd enhancing lesions | 0.2 | 1.4 | <0.0001
Relative reduction | 86%

Figure 1: Time to first relapse

16 HOW SUPPLIED/STORAGE AND HANDLING

16.1 How Supplied

PLEGRIDY (peginterferon beta-1a) injection is a sterile, preservative-free, clear to slightly opalescent and colorless to slightly yellow solution supplied as a 0.5 mL single-dose prefilled pen or a 0.5 mL single-dose prefilled syringe.

Subcutaneous Administration

PLEGRIDY (peginterferon beta-1a) injection for subcutaneous use is supplied as a single-dose prefilled pen or single-dose prefilled syringe with a rubber stopper and a 29-gauge, 0.5-inch staked needle with a rigid needle shield in the following packaging configurations:

- Carton containing two-125 mcg/0.5 mL single-dose prefilled pens of PLEGRIDY (NDC 64406-011-01).
- Starter Pack carton containing two single-dose prefilled pens; dose 1 provides 63 mcg/0.5 mL of PLEGRIDY and dose 2 provides 94 mcg/0.5 mL of PLEGRIDY (NDC 64406-012-01).
- Carton containing two-125 mcg/0.5 mL single-dose prefilled syringes of PLEGRIDY (NDC 64406-015-01).
- Starter Pack carton containing two single-dose prefilled syringes; dose 1 provides 63 mcg/0.5 mL of PLEGRIDY, and dose 2 provides 94 mcg/0.5 mL of PLEGRIDY (NDC 64406-016-01).

Intramuscular Administration

PLEGRIDY (peginterferon beta-1a) injection for intramuscular use is supplied as a single-dose prefilled syringe with a rubber stopper and a 23-gauge, 1.25-inch staked needle provided separately with the syringe in the following packaging configurations:

- Carton containing two-125 mcg/0.5 mL single-dose prefilled syringes of PLEGRIDY (NDC 64406-017-01).
- The PLEGRIDY Titration Kit must be prescribed and dispensed separately for treatment initiation. The Titration Kit contains two titration clips: The yellow clip (for dose 1) allows a delivered dose of 63 mcg of PLEGRIDY, and the purple clip (for dose 2) allows a delivered dose of 94 mcg of PLEGRIDY.

16.2 Storage and Handling

Store PLEGRIDY prefilled pens and prefilled syringes in a refrigerator between 2°C to 8°C (36°F to 46°F) in the closed original carton to protect from light until ready for injection. Do not freeze. Discard if frozen.

If refrigeration is unavailable, PLEGRIDY may be stored at room temperature up to 25°C (77°F) for a period up to 30 days, protected from light. PLEGRIDY can be removed from, and returned to, a refrigerator if necessary. The total combined time out of refrigeration should not exceed 30 days.

PLEGRIDY prefilled syringe for intramuscular administration contains natural rubber latex which may cause allergic reactions.

Dispose in a sharps-bin container or other hard plastic or metal sealable container. Always follow local regulations for disposal.

17 PATIENT COUNSELING INFORMATION

Advise the patient to read the FDA-approved patient labeling (Medication Guide and Instructions for Use).

Instructions for Self-Injection Technique and Procedures

Provide appropriate instruction for methods of self-injection, including careful review of the PLEGRIDY Medication Guide and Instructions for Use. Instruct patients in the use of aseptic technique when administering PLEGRIDY.

Inform patients that a healthcare provider should show them or their caregiver how to prepare to inject PLEGRIDY before administering the first dose. Tell patients not to re-use needles or syringes, and instruct patients on safe disposal procedures. Inform patients to dispose of used needles and syringes in a puncture-resistant container, and instruct patients regarding safe disposal of full containers.

Advise patients:

- to rotate areas of injection with each dose to minimize the likelihood of injection site reactions [see Warnings and Precautions (5.4)]. For subcutaneous administration, the usual injection sites are the abdomen, back of the upper arm, and thigh. For intramuscular administration, alternate injections between the left and right thigh.
- NOT to inject into an area of the body where the skin is irritated, reddened, bruised, infected, or scarred in any way
- to check the injection site after 2 hours for redness, swelling, and tenderness
- to contact their healthcare professional if they have a skin reaction and it does not clear up in a few days

Pregnancy

Advise patients to notify their healthcare provider if they become pregnant during treatment or plan to become pregnant [see Use in Specific Populations (8.1)].

Liver Disease

Advise patients that severe hepatic injury, including rare cases of hepatic failure, has been reported during the use of interferon beta. Advise patients of symptoms of hepatic dysfunction, and instruct patients to report them immediately to their physician [see Warnings and Precautions (5.1)].

Depression and Suicide

Advise patients that depression, suicidal ideation, and suicide have been reported with the use of interferon beta. Instruct patients to report symptoms of depression or thoughts of suicide to their physician immediately [see Warnings and Precautions (5.2)].

Anaphylaxis and Other Allergic Reactions

Advise patients of the symptoms of allergic reactions and anaphylaxis, and instruct patients to seek immediate medical attention if these symptoms occur. Inform latex-sensitive patients that the PLEGRIDY prefilled syringe for intramuscular administration contains natural rubber latex [see Warnings and Precautions (5.3)].

Injection Site Reactions Including Necrosis

Advise patients that injection site reactions can occur and that the reactions can include injection site necrosis. Instruct patients to report promptly any break in the skin that is associated with blue-black discoloration, swelling, or drainage of fluid from the injection site [see Warnings and Precautions (5.4)].

Cardiac Disease

Advise patients that worsening of significant cardiac disease has been reported in patients using interferon beta. Advise patients of symptoms of worsening cardiac condition, and instruct patients to report them immediately to their physician [see Warnings and Precautions (5.5)].

Pulmonary Arterial Hypertension

Inform patients that PAH has occurred in patients treated with interferon beta products, including PLEGRIDY. Instruct patients to promptly report any new symptoms such as new or increasing fatigue or shortness of breath to their healthcare provider [see Warnings and Precautions (5.8)].

Seizure

Advise patients that seizures have been reported in patients using PLEGRIDY. Instruct patients to report seizures immediately to their physician [see Warnings and Precautions (5.10)].

Flu-like Symptoms

Inform patients that flu-like symptoms are common following initiation of therapy with PLEGRIDY. Prophylactic and concurrent use of analgesics and/or antipyretics may prevent or ameliorate flu-like symptoms sometimes experienced during interferon treatment [see Dosage and Administration (2.3) and Adverse Reactions (6.1)].

43643-09

Manufactured by:
Biogen Inc.
Cambridge, MA 02142
U.S. License # 1697
1-800-456-2255
PLEGRIDY is a registered trademark of Biogen.
©2013-2023 Biogen

Medication Guide
PLEGRIDY® (PLEGG-rih-dee)
(peginterferon beta-1a)
injection, for subcutaneous or intramuscular use

Read this Medication Guide before you start using PLEGRIDY, and each time you get a refill. There may be new information. This information does not take the place of talking with your healthcare provider about your medical condition or your treatment.

What is the most important information I should know about PLEGRIDY?

PLEGRIDY can cause serious side effects, including:

- Liver problems or worsening of liver problems, including liver failure and death. Symptoms may include: yellowing of your skin or the white part of your eye, nausea, loss of appetite, tiredness, bleeding more easily than normal, confusion, sleepiness, dark colored urine, and pale stools.
  During your treatment with PLEGRIDY you will need to see your healthcare provider and have regular blood tests to check for these possible side effects.
- Depression or suicidal thoughts. Symptoms may include: new or worsening depression (feeling hopeless or bad about yourself), thoughts of hurting yourself or suicide, irritability (getting upset easily), nervousness, or new or worsening anxiety.
- Call your healthcare provider right away if you have any of the symptoms listed above.

What is PLEGRIDY?

- PLEGRIDY is a prescription medicine used to treat relapsing forms of multiple sclerosis (MS), to include clinically isolated syndrome, relapsing-remitting disease, and active secondary progressive disease, in adults.
- It is not known if PLEGRIDY is safe and effective in people under 18 or over 65 years of age.

Do not take PLEGRIDY if you:

- are allergic to interferon beta or peginterferon, or any of the other ingredients in PLEGRIDY. See the end of this Medication Guide for a complete list of ingredients in PLEGRIDY.

Before using PLEGRIDY, tell your healthcare provider about all of your medical conditions, including if you:

- are being treated for a mental illness or had treatment in the past for any mental illness, including depression and suicidal behavior.
- have or had liver problems.
- have or had low blood cell counts.
- have or had bleeding problems.
- have or had heart problems.
- have or had seizures (epilepsy).
- have or had thyroid problems.
- have or had any kind of autoimmune disease (where the body's immune system attacks the body's own cells).
- have or had an allergic reaction to rubber or latex. The tip of the cap of the PLEGRIDY prefilled syringe for intramuscular use is made of natural rubber latex.
- are pregnant or plan to become pregnant. It is not known if PLEGRIDY can harm your unborn baby. Tell your healthcare provider if you become pregnant during your treatment with PLEGRIDY.
- are breastfeeding or plan to breastfeed. PLEGRIDY may pass into your breastmilk. Talk to your healthcare provider about the best way to feed your baby if you use PLEGRIDY.

Tell your healthcare provider about all the medicines you take, including prescription and over-the-counter medicines, vitamins, and herbal supplements.

How should I use PLEGRIDY?

- See the detailed Instructions for Use for instructions on how to prepare and inject your dose of PLEGRIDY.
- Use PLEGRIDY exactly as your healthcare provider tells you. A healthcare provider should show you how to inject your PLEGRIDY before you use it for the first time.
- Your healthcare provider will tell you how much PLEGRIDY to inject and how often to inject PLEGRIDY. Do not inject more than your healthcare provider tells you to.
- When you use PLEGRIDY for the first time, your healthcare provider may tell you to slowly increase your dose.
- If you are prescribed PLEGRIDY for injection under the skin (subcutaneous injection):
  - you should use a PLEGRIDY Starter Pack to slowly adjust your dose when you begin treatment.
  - inject PLEGRIDY under the skin of your stomach (abdomen), back of upper arm, or thigh 1 time every 14 days.
- If you are prescribed PLEGRIDY for injection into the muscle (intramuscular injection):
  - you should use a PLEGRIDY Titration Kit to slowly adjust your dose when you begin treatment.
  - inject PLEGRIDY into your thigh 1 time every 14 days.
- If your healthcare provider changes where you are injecting PLEGRIDY (under the skin or into the muscle), you do not need to slowly increase your dose again.
- Change (rotate) the site you choose with each injection to help decrease the chance that you will have an injection site reaction. Do not inject into an area of the body where the skin is irritated, reddened, bruised, infected, or scarred in any way.
- After 2 hours check your injection site for redness, pain, itching, swelling, tenderness, a break in your skin that becomes blue and black, or drains fluid. If you have a skin reaction and it does not clear up in a few days, contact your healthcare provider.
- Always use a new, PLEGRIDY prefilled pen or new, unopened single dose prefilled syringe for each injection.

What are the possible side effects of PLEGRIDY?

See “What is the most important information I should know about PLEGRIDY?”
PLEGRIDY may cause serious side effects, including:

- serious allergic reactions. Serious allergic reactions can happen if you take PLEGRIDY. Symptoms may include: itching, swelling of the face, eyes, lips, tongue, or throat, trouble breathing, feeling faint, anxiousness, skin rash, hives, skin bumps. Get emergency help right away if you have any of these symptoms. Talk to your healthcare provider before taking another dose of PLEGRIDY.
- injection site reactions. PLEGRIDY may commonly cause redness, pain, itching, or swelling at the place where your injection was given. Call your healthcare provider right away if an injection site becomes swollen and painful or the area looks infected. You may have a skin infection or an area of severe skin damage (necrosis) requiring treatment by a healthcare provider.
- heart problems, including congestive heart failure. Call your healthcare provider right away if you have worsening symptoms of heart failure such as shortness of breath or swelling of your lower legs or feet while using PLEGRIDY.
  - Some people using PLEGRIDY may have other heart problems, including low blood pressure, fast or abnormal heart beat, chest pain, heart attack, or a heart muscle problem (cardiomyopathy).
- blood problems and changes in your blood tests. PLEGRIDY can decrease your white blood cells or platelets, which can cause an increased risk of infection, bleeding, or anemia and can cause changes in your liver function tests. Your healthcare provider will do tests to monitor for side effects while you use PLEGRIDY.
- thrombotic microangiopathy (TMA). TMA is a condition that involves injury to the smallest blood vessels in your body. TMA can also cause injury to your red cells (the cells that carry oxygen to your organs and tissues) and your platelets (cells that help your blood clot) and can sometimes lead to death. Your healthcare provider may tell you to stop taking PLEGRIDY if you develop TMA.
- pulmonary arterial hypertension. Pulmonary arterial hypertension can occur with interferon beta products, including PLEGRIDY. Symptoms may include new or increasing fatigue or shortness of breath. Contact your healthcare provider right away if you develop these symptoms.
- autoimmune diseases. Problems with easy bleeding or bruising (idiopathic thrombocytopenia), thyroid gland problems (hyperthyroidism and hypothyroidism), and autoimmune hepatitis have happened in some people who use interferon beta.
- seizures. Some people have had seizures while taking PLEGRIDY, including people who have never had seizures before.

The most common side effects of PLEGRIDY include:

- flu-like symptoms. Many people who use PLEGRIDY have flu-like symptoms, especially early in the course of therapy. These symptoms are not really the flu. You cannot pass it on to anyone else.
  - You may be able to manage these flu-like symptoms by taking over-the-counter pain and fever reducers and drinking plenty of water.

Flu-like symptoms or other common side effects of PLEGRIDY may include: headache, muscle and joint aches, fever, chills, or tiredness.
These are not all the possible side effects of PLEGRIDY.
Call your doctor for medical advice about side effects. You may report side effects to FDA at 1-800-FDA-1088.

General Information about the safe and effective use of PLEGRIDY.

Medicines are sometimes prescribed for purposes other than those listed in a Medication Guide. Do not use PLEGRIDY for a condition for which it was not prescribed. Do not give PLEGRIDY to other people, even if they have the same symptoms that you have. It may harm them. You can ask your pharmacist or healthcare provider for information about PLEGRIDY that is written for health professionals.

What are the ingredients in PLEGRIDY?

Active ingredient: peginterferon beta-1a.

Inactive ingredients:

- Single-dose Prefilled Pen (subcutaneous injection only): L-arginine hydrochloride, glacial acetic acid, polysorbate 20, and sodium acetate trihydrate in sterile water for injection.
- Single-dose Prefilled Syringe (subcutaneous and intramuscular injection): L-arginine hydrochloride, glacial acetic acid, polysorbate 20, and sodium acetate trihydrate in sterile water for injection.

For more information, go to www.plegridy.com or call 1-800-456-2255.
Manufactured by: Biogen Inc., Cambridge, MA 02142, U.S. License # 1697
PLEGRIDY is a registered trademark of Biogen. ©2013-2023 Biogen

This Medication Guide has been approved by the U.S. Food and Drug Administration.

Revised: 7/2023

Instructions for Use

PLEGRIDY® (PLEGG-rih-dee)

(peginterferon beta-1a) injection, for Subcutaneous Use

Single-Dose Prefilled Pen

Starter Pack

Important: Do not remove the Plegridy Pen cap until you are ready to inject.

How to Inject your Plegridy Pen

Read this Instructions for Use before you start using Plegridy and each time you get a refill of your prescription. There may be new information. This information does not take the place of talking to your healthcare provider about your medical condition or your treatment.

Note:

- Before you use your Plegridy Pen for the first time, your healthcare provider should show you or your caregiver how to prepare and inject your Plegridy Pen the right way.
- If you experience difficulty or have questions, call 1-800-456-2255.
- Plegridy Pen is for use under the skin only (subcutaneous).
- Each Plegridy Pen can be used 1 time only. Do not share your Plegridy Pen with anyone else. By sharing the Pen, you may give an infection to them or get an infection from them.
- Take your Plegridy Pen out of the refrigerator and let it come to room temperature for at least 30 minutes before your injection.
- Do not use more than 1 Plegridy Pen every 14 days.
- Do not use your Plegridy Pen if it has been dropped or is visibly damaged.

How should I store Plegridy?

- Store Plegridy in the refrigerator between 36°F to 46°F (2°C to 8°C).
- If a refrigerator is not available, PLEGRIDY may be stored at room temperature up to 77°F (25°C) for up to 30 days in total.
- Keep Plegridy in the original carton to protect it from light.
- Do not freeze Plegridy.
- Keep Plegridy Pens, needles, and all medicines out of the reach of children.

Supplies needed for your Starter Pack for Plegridy Pen injection (See Figure A):

- 1 Starter Pack for Plegridy Pen which contains:
  - 1 Plegridy 63 mcg Pen (orange pen)
  - 1 Plegridy 94 mcg Pen (blue pen)

Additional supplies which are not included in the pack (See Figure B):

- alcohol wipe
- gauze pad
- adhesive bandage
- 1 sharps container for throwing away used needles and Plegridy Pens. See “Disposing of your used Plegridy Pens” at the end of these instructions.
- a well-lit area and a clean, flat surface to work on, like a table

Dose Schedule

- Choose the right Plegridy Pen for your dose. The Starter Pack for Plegridy Pen contains your first 2 injections to slowly adjust your dose.

When | Which Dose | Choose
Day 1 (63 mcg) | First Dose: 63 mcg | Orange Pen (See Figure C)
When | Which Dose | Choose
Day 15 (94 mcg) | Second Dose: 94 mcg | Blue Pen (See Figure D)

- Make sure you use the 63 mcg orange pen for your first dose (on day 1).
- Make sure you use the 94 mcg blue pen for your second dose (on day 15).

Ask your healthcare provider which Plegridy Pen you should use for your correct dose if you are not sure.

Before Use – Parts of your Plegridy Pen before use (See Figure E):

Important: Do not remove the Plegridy Pen cap until you are ready to inject. If you remove the cap before you are ready to inject, do not re-cap the pen. Re-capping could cause the pen to lock.

Preparing for your injection:

Step 1: Take your Plegridy Pen out of the refrigerator and let it come to room temperature for at least 30 minutes.

- Do not use external heat sources such as hot water to warm your Plegridy Pen.

Step 2: Collect your supplies and wash your hands

- Find a well-lit area and a clean, flat surface like a table and collect all the supplies you will need to give yourself or to receive an injection.
- Wash your hands with soap and water.

Step 3: Check your Plegridy Pen (see Figure F)

- Check the injection status window on your Plegridy Pen. Before you give your injection, you should see green stripes in the injection status window.
  - Do not use Plegridy Pen if you do not see the green stripes in the injection status window.

- Check the expiration date printed on your Plegridy Pen.
  - Do not use Plegridy Pen past the expiration date.

- Check the medicine window on your Plegridy Pen and make sure the Plegridy medicine is clear and colorless.
  - Do not use Plegridy Pen if the liquid is colored, cloudy, or has floating particles in it.
  - You might see air bubbles in the medicine window. This is normal and will not affect your dose.

Step 4: Choose and clean your injection site

- Plegridy Pen is for use under the skin only (subcutaneous).
- Plegridy Pen should be injected into your thigh, stomach area (abdomen) or the back of your upper arm (See Figure G).
  - Do not inject into an area of your body where the skin is irritated, reddened, bruised, infected or scarred.
- Change (rotate) your injection site for each injection. Do not use the same injection site for each injection.
- Choose an injection site and wipe your skin with an alcohol wipe.
  - Do not touch this area again before giving your injection.
- Let your injection site dry on its own before injecting your dose.

Giving your injection:
Step 5: Remove the Plegridy Pen cap

- Pull the Plegridy Pen cap straight off and set it aside (See Figure H).
  - The needle is covered by the needle cover and the needle will not be seen.
- Important information:
  - Do not touch or clean the needle cover. You could get a needle stick injury or the pen may lock.
  - Do not recap your Plegridy Pen. This could lock the pen.
- Your Plegridy Pen is ready to inject after the cap is removed.

Figure H

Step 6: Give your injection

- Place your Plegridy Pen on your chosen injection site.
  - You should hold your Plegridy Pen at a 90o angle to your injection site so that you can see the green stripes in the injection status window (See Figure I).
  - Do not use your Plegridy Pen unless you see green stripes in the injection status window.
    Note: Be ready to inject before you start pressing your Plegridy Pen down on your injection site. After you start pressing, the needle cover will lock when it is lifted from the site.
- Firmly press and hold down your Plegridy Pen on your injection site. This will insert the needle and start your injection (See Figure J).
  - You will hear a clicking sound.
- Continue to hold your Plegridy Pen firmly down on your injection site until the clicking sound has stopped (See figure K).
  - Do not lift your Plegridy Pen off your injection site until the clicking sound stops and you see green checkmarks in the injection status window.

If you do not hear clicking sounds, or you do not see green checkmarks in the injection status window after trying to give your injection, your Plegridy Pen may have locked and you should call 1-800-456-2255 for help.
Step 7: Remove your Plegridy Pen from your injection site

- After the clicking sound has stopped, lift your Plegridy Pen from your injection site. The needle will be covered by the needle cover and it will lock (see Figure L).

Step 8: Check to make sure you have received your full dose of Plegridy (see Figure M)

- Check the injection status window. You should see green checkmarks in the injection status.
- Check the medicine window. You should see a yellow plunger in the medicine.
  - If you see blood at your injection site, wipe it off with the gauze pad and apply an adhesive bandage.

After your injection:

After Use – Parts of your Plegridy Pen (Figure N)

Important: Do not touch the needle cover in any way. You could get a needle stick injury.

Note: After the pen has been removed from the injection site, the needle cover will lock to protect against needle stick injury. Do not recap your Plegridy Pen.

Step 9: Disposing of your used Plegridy Pens

- Put your used Plegridy Pens in a FDA-cleared sharps disposal container right away after use. Do not throw away (dispose of) Plegridy Pens in your household trash.
- If you do not have a FDA-cleared sharps disposal container, you may use a household container that is:
  - made of a heavy-duty plastic,
  - can be closed with a tight-fitting, puncture-resistant lid, without sharps being able to come out,
  - upright and stable during use,
  - leak resistant, and
  - properly labeled to warn of hazardous waste inside the container.
- When your sharps disposal container is almost full, you will need to follow your community guidelines for the right way to dispose of your sharps disposal container. There may be state or local laws about how you should throw away used needles and pens. For more information about safe sharps disposal, and for specific information about sharps disposal in the state that you live in, go to the FDA's website at: http://www.fda.gov/safesharpsdisposal.
- Do not dispose of your used sharps disposal container in your household trash unless your community guidelines permit this. Do not recycle your used sharps disposal container.
- Do not recap your Plegridy Pen.

Step 10: Check your injection site

- Plegridy may commonly cause redness, pain or swelling of your skin at the injection site.
- After 2 hours check your injection site for redness, swelling or tenderness.
- Call your healthcare provider right away if your injection site becomes swollen and painful or the area looks infected and does not heal within a few days.

Questions?

For product or service-related questions, call 1-800-456-2255 or go to www.plegridy.com.

This Instructions for Use has been approved by the U.S. Food and Drug Administration.

Manufactured by: Biogen Inc., Cambridge, MA 02142, U.S. License # 1697

©2013-2022 Biogen. All rights reserved. 1-800-456-2255

Issued: 03/2020

43839-03

Instructions for Use

PLEGRIDY® (PLEGG-rih-dee)

(peginterferon beta-1a) injection, for Subcutaneous Use

Single-Dose Prefilled Pen

125 mcg

Important: Do not remove the Plegridy Pen cap until you are ready to inject.

How to Inject your Plegridy Pen

Read this Instructions for Use before you start using Plegridy and each time you get a refill of your prescription. There may be new information. This information does not take the place of talking to your healthcare provider about your medical condition or your treatment.

Note:

- Before you use your Plegridy Pen for the first time, your healthcare provider should show you or your caregiver how to prepare and inject your Plegridy Pen the right way.
- If you experience difficulty or have questions, call 1-800-456-2255.
- Plegridy Pen is for use under the skin only (subcutaneous).
- Each Plegridy Pen can be used 1 time only. Do not share your Plegridy Pen with anyone else. By sharing the Pen, you may give an infection to them or get an infection from them.
- Take your Plegridy Pen out of the refrigerator and let it come to room temperature for at least 30 minutes before your injection.
- Do not use more than 1 Plegridy Pen every 14 days.
- Do not use your Plegridy Pen if it has been dropped or is visibly damaged.

How should I store Plegridy?

- Store Plegridy in the refrigerator between 36°F to 46°F (2°C to 8°C).
- If a refrigerator is not available, PLEGRIDY may be stored at room temperature up to 77°F (25°C) for up to 30 days in total.
- Keep Plegridy in the original carton to protect it from light.
- Do not freeze Plegridy.
- Keep Plegridy Pens, needles, and all medicines out of the reach of children.

Supplies needed for your Plegridy Pen injection:

- 1 Plegridy 125 mcg Pen (see Figure A)

Before Use – Parts of your Plegridy Pen (Figure A)

Important: Do not remove the Plegridy Pen cap until you are ready to inject. If you remove the cap before you are ready to inject, do not re-cap the pen. Re-capping could cause the pen to lock.

Additional supplies which are not included in the pack (See Figure B):

- alcohol wipe
- gauze pad
- adhesive bandage
- 1 sharps container for throwing away used needles and Plegridy Pens. See “Disposing of your used Plegridy Pens” at the end of these instructions.
- a well-lit area and a clean, flat surface to work on, like a table

Preparing for your injection:

Step 1: Take your Plegridy Pen out of the refrigerator and let it come to room temperature for at least 30 minutes.

- Do not use external heat sources such as hot water to warm your Plegridy Pen.

Step 2: Collect your supplies and wash your hands

- Find a well-lit area and a clean, flat surface like a table and collect all the supplies you will need to give yourself or to receive an injection.
- Wash your hands with soap and water.

Step 3: Check your Plegridy Pen (see Figure C)

- Check the injection status window on your Plegridy Pen. Before you give your injection, you should see green stripes in the injection status window.
  - Do not use Plegridy Pen if you do not see the green stripes in the injection status window.

- Check the expiration date printed on your Plegridy Pen.
  - Do not use Plegridy Pen past the expiration date.

- Check the medicine window on your Plegridy Pen and make sure the Plegridy medicine is clear and colorless.
  - Do not use Plegridy Pen if the liquid is colored, cloudy, or has floating particles in it.
  - You might see air bubbles in the medicine window. This is normal and will not affect your dose.

Step 4: Choose and clean your injection site

- Plegridy Pen is for use under the skin only (subcutaneous).
- Plegridy Pen should be injected into your thigh, abdomen or the back of your upper arm (See Figure D).
  - Do not inject into an area of your body where the skin is irritated, reddened, bruised, infected or scarred.
- Change (rotate) your injection site for each injection. Do not use the same injection site for each injection.
- Choose an injection site and wipe your skin with an alcohol wipe.
  - Do not touch this area again before giving your injection.
- Let your injection site dry on its own before injecting your dose.

Giving your injection:
Step 5: Remove the Plegridy Pen cap

- Pull the Plegridy Pen cap straight off and set it aside (See Figure E).
  - The needle is covered by the needle cover and the needle will not be seen.
- Important information:
  - Do not touch or clean the needle cover. You could get a needle stick injury or the pen may lock.
  - Do not recap your Plegridy Pen. This could lock the pen.
- Your Plegridy Pen is ready to inject after the cap is removed.

Step 6: Give your injection

- Place your Plegridy Pen on your chosen injection site.
  - You should hold your Plegridy Pen at a 90o angle to your injection site so that you can see the green stripes in the injection status window (See Figure F).
  - Do not use your Plegridy Pen unless you see green stripes in the injection status window.
    Note: Be ready to inject before you start pressing your Plegridy Pen down on your injection site. After you start pressing, the needle cover will lock when it is lifted from the site.
- Firmly press and hold down your Plegridy Pen on your injection site. This will insert the needle and start your injection (See Figure G).
  - You will hear a clicking sound.
- Continue to hold your Plegridy Pen firmly down on your injection site until the clicking sound has stopped (see Figure H).
  - Do not lift your Plegridy Pen off your injection site until the clicking sound stops and you see green checkmarks in the injection status window.

If you do not hear clicking sounds or you do not see green checkmarks in the injection status window after trying to give your injection, your Plegridy Pen may have locked and you should call 1-800-456-2255.
Step 7: Remove your Plegridy Pen from your injection site

- After the clicking sound has stopped, lift your Plegridy Pen from your injection site. The needle will be covered and it will lock (see Figure I).
  Step 8: Check and make sure you received your full dose of Plegridy (see Figure J)

- Check the injection status window. You should see green checkmarks in the injection status window.
- Check the medicine window. You should see a yellow plunger in the medicine window.
  - If you see blood at your injection site, wipe it off with gauze and apply an adhesive bandage.

After your injection:

After Use – Parts of your Plegridy Pen (Figure K)

Important: Do not touch the needle cover in any way. You could get a needle stick injury.

Note: After the pen has been removed from the injection site, the needle cover will lock to protect against needle stick injury. Do not recap your Plegridy Pen.

Step 9: Disposing of your used Plegridy Pens

- Put your used Plegridy Pens in an FDA-cleared sharps disposal container right away after use. Do not throw away (dispose of) Plegridy Pens in your household trash.
- If you do not have an FDA-cleared sharps disposal container, you may use a household container that is:
  - made of a heavy-duty plastic,
  - can be closed with a tight-fitting, puncture-resistant lid, without sharps being able to come out,
  - upright and stable during use,
  - leak resistant, and
  - properly labeled to warn of hazardous waste inside the container.
- When your sharps disposal container is almost full, you will need to follow your community guidelines for the right way to dispose of your sharps disposal container. There may be state or local laws about how you should throw away used needles and pens. For more information about safe sharps disposal, and for specific information about sharps disposal in the state that you live in, go to the FDA's website at: http://www.fda.gov/safesharpsdisposal.
- Do not dispose of your used sharps disposal container in your household trash unless your community guidelines permit this. Do not recycle your used sharps disposal container.
- Do not recap your Plegridy Pen.

Step 10: Check your injection site

- Plegridy may commonly cause redness, pain or swelling of your skin at the injection site.
- After 2 hours, check your injection site for redness, swelling or tenderness. Call your healthcare provider right away if your injection site becomes swollen and painful or the area looks infected and does not heal within a few days.

Questions?

For product or service-related questions, call 1-800-456-2255 or go to www.plegridy.com.

This Instructions for Use has been approved by the U.S. Food and Drug Administration.

Manufactured by: Biogen Inc., Cambridge, MA 02142, U.S. License # 1697

©2013-2020 Biogen. All rights reserved. 1-800-456-2255

Issued: 03/2020

43644-03

Instructions for Use

PLEGRIDY® (PLEGG-rih-dee)

(peginterferon beta-1a) injection for Subcutaneous Use

Single-Dose Prefilled Syringe

Starter Pack

How to Inject your Plegridy Prefilled Syringe

Read this Instructions for Use before you start using Plegridy and each time you get a refill of your prescription. There may be new information. This information does not take the place of talking to your healthcare provider about your medical condition or your treatment.

Note:

- Before you use your Plegridy Prefilled Syringe for the first time, your healthcare provider should show you or your caregiver how to prepare and inject your Plegridy Prefilled Syringe the right way.
- If you experience difficulty or have questions, call 1-800-456-2255.
- Plegridy Prefilled Syringe is for use under the skin only (subcutaneous).
- Each Plegridy Prefilled Syringe can be used 1 time only. Do not share your Plegridy Prefilled Syringe with anyone else. By sharing the needle, you may give an infection to them or get an infection from them.
- Take your Plegridy Prefilled Syringe out of the refrigerator and let it come to room temperature for at least 30 minutes before your injection.
- Do not use more than 1 Plegridy Prefilled Syringe every 14 days.
- Do not use your Plegridy Prefilled Syringe if it has been dropped or is visibly damaged.

How should I store Plegridy?

- Store Plegridy in the refrigerator between 36°F to 46°F (2°C to 8°C).
- If a refrigerator is not available, PLEGRIDY may be stored at room temperature up to 77°F (25°C) for up to 30 days in total.
- Keep Plegridy in the original carton to protect it from light.
- Do not freeze Plegridy.
- Keep Plegridy Prefilled Syringes, needles, and all medicines out of the reach of children.

Supplies needed for your Starter Pack for Plegridy Prefilled Syringe injection (See Figure A):

- 1 Starter Pack for Plegridy Prefilled Syringe which contains:
  - 1 Plegridy 63 mcg Prefilled Syringe (orange syringe)
  - 1 Plegridy 94 mcg Prefilled Syringe (blue syringe)

Additional supplies which are not included in the pack (See Figure B):

- alcohol wipe
- gauze pad
- adhesive bandage
- 1 sharps container for throwing away used needles and Plegridy Prefilled Syringes. See “Disposing of your used Plegridy Prefilled Syringes” at the end of these instructions.
- a well-lit area and a clean, flat surface to work on, like a table

Dose Schedule

- Choose the right Plegridy Prefilled Syringe for your dose. The Starter Pack for Plegridy Prefilled Syringe contains your first 2 injections to slowly adjust your dose.

When | Which Dose | Choose
Day 1 | First Dose: | Orange Syringe (See Figure C)
(63 mcg) | 63 mcg
When | Which Dose | Choose
Day 15 | Second Dose: | Blue Syringe (See Figure D)
(94 mcg) | 94 mcg

- Make sure you use the 63 mcg orange syringe for your first dose (on day 1).
- Make sure you use the 94 mcg blue syringe for your second dose (on day 15).

Ask your healthcare provider which Plegridy Prefilled Syringe you should use for your correct dose if you are not sure.

Parts of your Plegridy Prefilled Syringe (See Figure E):

Preparing for your injection:

Step 1: Take your Plegridy Prefilled Syringe out of the refrigerator and let it come to room temperature for at least 30 minutes.

- Do not use external heat sources such as hot water to warm your Plegridy Prefilled Syringe.

Step 2: Collect your supplies and wash your hands

- Find a well-lit area and a clean, flat surface like a table and collect all the supplies you will need to give yourself or to receive an injection.
- Wash your hands with soap and water.

Step 3: Check your Plegridy Prefilled Syringe

Check the expiration date printed on your Plegridy Prefilled Syringe (See Figure F).

- Do not use Plegridy Prefilled Syringe past the expiration date.

- Check that your Plegridy medicine is clear and colorless (See Figure G).
  - Do not use Plegridy Prefilled Syringe if the liquid is colored, cloudy, or has floating particles in it.
  - You might see air bubbles in your Plegridy medicine. This is normal and will not affect your dose.

Step 4: Choose and clean your injection site

- Plegridy Prefilled Syringe is for use under the skin only (subcutaneous).
- Plegridy Prefilled Syringe should be injected into your thigh, stomach area (abdomen) or the back of your upper arm (See Figure H).
  - Do not inject directly into your belly button.
  - Do not inject into an area of your body where the skin is irritated, reddened, bruised, infected or scarred.
- Change (rotate) your injection site for each injection. Do not use the same injection site for each injection.
- Choose an injection site and wipe your skin with an alcohol wipe.
  - Do not touch this area again before giving your injection.
- Let your injection site dry on its own before injecting the dose.
- Do not take off the Plegridy Prefilled Syringe needle cover until you are ready to inject.

Giving Your Injection:
Step 5: Remove the Plegridy Prefilled Syringe needle cover

- With 1 hand, hold your Plegridy Prefilled Syringe. With your other hand, firmly hold the needle cover and pull the needle cover straight off the needle (See Figure I).
  - Be careful when removing the needle cover to avoid getting a needle stick injury.
  - Do not touch the needle.
  - Important: Do not recap the Plegridy Prefilled Syringe. You could get a needle stick injury.
  - Throw away the needle cover after your injection.

Step 6: Gently pinch the injection site

- With 1 hand, use your thumb and first finger and pinch the skin around your cleaned injection site (See Figure J).

Step 7: Give your Plegridy Prefilled Syringe injection

- With your other hand, hold your Plegridy Prefilled Syringe like a pencil. Use a quick dart-like motion and insert the needle at a 90° angle into your skin (See Figure K).
- After the needle is in, let go of your skin.

- Slowly push the plunger down until the syringe is empty (See Figure L).
  - Do not take your Plegridy Prefilled Syringe out of your injection site until you have slowly pushed the plunger all the way down.

- Pull the needle straight out of your skin (See Figure M).
  - If you see blood at your injection site, wipe it off with the gauze pad and apply an adhesive bandage.
- Important: Do not recap your Plegridy Prefilled Syringe. You could get a needle stick injury.
- Do not reuse your Plegridy Prefilled Syringe.

After Your Injection:

Step 8: Disposing of your used Plegridy Prefilled Syringes

- Put your used Plegridy Prefilled Syringes in a FDA-cleared sharps disposal container right away after use. Do not throw away (dispose of) Plegridy Prefilled Syringes in your household trash.
- If you do not have a FDA-cleared sharps disposal container, you may use a household container that is:
  - made of a heavy-duty plastic,
  - can be closed with a tight-fitting, puncture-resistant lid, without sharps being able to come out,
  - upright and stable during use,
  - leak resistant, and
  - properly labeled to warn of hazardous waste inside the container.
- When your sharps disposal container is almost full, you will need to follow your community guidelines for the right way to dispose of your sharps disposal container. There may be state or local laws about how you should throw away used needles and syringes. For more information about safe sharps disposal, and for specific information about sharps disposal in the state that you live in, go to the FDA's website at: http://www.fda.gov/safesharpsdisposal.
- Do not dispose of your used sharps disposal container in your household trash unless your community guidelines permit this. Do not recycle your used sharps disposal container.

Step 9: Check your injection site

- Plegridy may commonly cause redness, pain or swelling of your skin at the injection site.
- After 2 hours check your injection site for redness, swelling or tenderness.
- Call your healthcare provider right away if your injection site becomes swollen and painful or the area looks infected and does not heal within a few days.

Questions?

For product or service-related questions, call 1-800-456-2255 or go to www.plegridy.com.

This Instructions for Use has been approved by the U.S. Food and Drug Administration.

Manufactured by: Biogen Inc., Cambridge, MA 02142, U.S. License # 1697

©2013-2020 Biogen. All rights reserved. 1-800-456-2255

Issued: 03/2020

43840-05

INSTRUCTIONS FOR USE

PLEGRIDY® (PLEGG-rih-dee)

(peginterferon beta-1a) injection, for Subcutaneous Use

Single-Dose Prefilled Syringe

125 mcg

How to Inject your Plegridy Prefilled Syringe

Read this Instructions for Use before you start using Plegridy and each time you get a refill of your prescription. There may be new information. This information does not take the place of talking to your healthcare provider about your medical condition or your treatment.

Important Information

Follow this Instructions for Use for the Plegridy prefilled syringe for subcutaneous use (under the skin). There is a different Instructions for Use for the Plegridy prefilled syringe for intramuscular use (into the muscle).

Note:

- Before you use your Plegridy Prefilled Syringe for the first time, your healthcare provider should show you or your caregiver how to prepare and inject your Plegridy Prefilled Syringe the right way.
- If you experience difficulty or have questions, call 1-800-456-2255.
- Plegridy Prefilled Syringe is for use under the skin only (subcutaneous).
- Each Plegridy Prefilled Syringe can be used 1 time only. Do not share your Plegridy Prefilled Syringe with anyone else. By sharing the needle, you may give an infection to them or get an infection from them.
- Take your Plegridy Prefilled Syringe out of the refrigerator and let it come to room temperature for at least 30 minutes before your injection.
- Do not use more than 1 Plegridy Prefilled Syringe every 14 days.
- Do not use your Plegridy Prefilled Syringe if it has been dropped or is visibly damaged.

How should I store Plegridy?

- Store Plegridy in the refrigerator between 36°F to 46°F (2°C to 8°C).
- If a refrigerator is not available, PLEGRIDY may be stored at room temperature up to 77°F (25°C) for up to 30 days in total.
- Keep Plegridy in the original carton to protect it from light.
- Do not freeze Plegridy.
- Keep Plegridy Prefilled Syringes, needles, and all medicines out of the reach of children.

Supplies needed for your Plegridy Prefilled Syringe injection:

- 1 Plegridy 125 mcg Prefilled Syringe (See Figure A)

Additional supplies which are not included in the pack (See Figure B):

- alcohol wipe
- gauze pad
- adhesive bandage
- 1 sharps container for throwing away used needles and Plegridy Prefilled Syringes. See “Disposing of your used Plegridy Prefilled Syringes” at the end of these instructions.
- a well-lit area and a clean, flat surface to work on, like a table

Preparing for your injection:

Step 1: Take your Plegridy Prefilled Syringe out of the refrigerator and let it come to room temperature for at least 30 minutes.

- Do not use external heat sources such as hot water to warm your Plegridy Prefilled Syringe.

Step 2: Collect your supplies and wash your hands

- Find a well-lit area and a clean, flat surface like a table and collect all the supplies you will need to give yourself or to receive an injection.
- Wash your hands with soap and water.

Step 3: Check your Plegridy Prefilled Syringe

- Check the expiration date printed on your Plegridy Prefilled Syringe (See Figure C).
  - Do not use Plegridy Prefilled Syringe past the expiration date.

- Check that your Plegridy medicine is clear and colorless (See Figure D).
  - Do not use Plegridy Prefilled Syringe if the liquid is colored, cloudy, or has floating particles in it.
  - You might see air bubbles in your Plegridy medicine. This is normal and will not affect your dose.

Step 4: Choose and clean your injection site

- Plegridy Prefilled Syringe is for use under the skin only (subcutaneous).
- Plegridy Prefilled Syringe should be injected into your thigh, abdomen or the back of your upper arm (See Figure E).
  - Do not inject directly into your belly button.
  - Do not inject into an area of your body where the skin is irritated, reddened, bruised, infected or scarred.
- Change (rotate) your injection site for each injection. Do not use the same injection site for each injection.
- Choose an injection site and wipe your skin with an alcohol wipe.
- Do not touch this area again before giving your injection.
- Let your injection site dry on its own before injecting your dose.
- Do not take off the Plegridy Prefilled Syringe needle cover until you are ready to inject.

Giving Your Injection:
Step 5: Remove the Plegridy Prefilled Syringe needle cover

- With 1 hand, hold your Plegridy Prefilled Syringe. With your other hand, firmly hold the needle cover and pull the needle cover straight off the needle (See Figure F).
  - Be careful when removing the needle cover to avoid getting a needle stick injury.
  - Do not touch the needle.
  - Important: Do not recap the Plegridy Prefilled Syringe. You could get a needle stick injury.
  - Throw away the needle cover after your injection.

Step 6: Gently pinch the injection site

- With 1 hand, use your thumb and first finger and pinch the skin around your cleaned injection site (See Figure G).

Step 7: Give your Plegridy Prefilled Syringe injection

- With your other hand, hold your Plegridy Prefilled Syringe like a pencil. Use a quick dart-like motion and insert the needle at a 90° angle into your skin (See Figure H).
- After the needle is in, let go of your skin.

- Slowly push the plunger down until the syringe is empty (See Figure I).
  - Do not take your Plegridy Prefilled Syringe out of your injection site until you have slowly pushed the plunger all the way down.

- Pull the needle straight out of your skin (See Figure J).
  - If you see blood at your injection site, wipe it off with gauze and apply an adhesive bandage.
- Important: Do not recap your Plegridy Prefilled Syringe. You could get a needle stick injury.
- Do not reuse your Plegridy Prefilled Syringe.

After Your Injection:

Step 8: Disposing of your used Plegridy Prefilled Syringes

- Put your used Plegridy Prefilled Syringes in an FDA-cleared sharps disposal container right away after use. Do not throw away (dispose of) Plegridy Prefilled Syringes in your household trash.
- If you do not have a FDA-cleared sharps disposal container, you may use a household container that is:
  - made of a heavy-duty plastic,
  - can be closed with a tight-fitting, puncture-resistant lid, without sharps being able to come out,
  - upright and stable during use,
  - leak resistant, and
  - properly labeled to warn of hazardous waste inside the container.
- When your sharps disposal container is almost full, you will need to follow your community guidelines for the right way to dispose of your sharps disposal container. There may be state or local laws about how you should throw away used needles and syringes. For more information about safe sharps disposal, and for specific information about sharps disposal in the state that you live in, go to the FDA's website at: http://www.fda.gov/safesharpsdisposal.
- Do not dispose of your used sharps disposal container in your household trash unless your community guidelines permit this. Do not recycle your used sharps disposal container.

Step 9: Check your injection site

- Plegridy may commonly cause redness, pain or swelling of your skin at the injection site.
- After 2 hours, check your injection site for redness, swelling or tenderness.
- Call your healthcare provider right away if your injection site becomes swollen and painful or the area looks infected and does not heal within a few days.

Questions?

For product or service-related questions, call 1-800-456-2255 or go to www.plegridy.com.

This Instructions for Use has been approved by the U.S. Food and Drug Administration.

Manufactured by: Biogen Inc., Cambridge, MA 02142, U.S. License # 1697
©2013-2021 Biogen. All rights reserved. 1-800-456-2255

Issued: 1/2021
43654-04

Instructions for Use

PLEGRIDY® (PLEGG-rih-dee)

(peginterferon beta-1a)

injection for intramuscular use

Single-Dose Prefilled Syringe

Read this Instructions for Use before you start using Plegridy and each time you get a refill. There may be new information. This information does not take the place of talking to your healthcare provider about your medical condition or your treatment.

Important information:

- The tip of the cap of the Plegridy prefilled syringe is made of natural rubber latex. Tell your healthcare provider if you are allergic to rubber or latex.
- Follow this Instructions for Use for the Plegridy prefilled syringe for intramuscular use (into the muscle). There is a different Instructions for Use for the Plegridy prefilled syringe for subcutaneous use (under the skin).

Note:

- Before you use your Plegridy prefilled syringe for the first time, your healthcare provider should show you or your caregiver how to prepare and inject your Plegridy prefilled syringe the right way.
- Each Plegridy prefilled syringe can be used 1 time only. Do not share your Plegridy prefilled syringe with anyone else. By sharing the needle, you may give an infection to them or get an infection from them.
- Do not use more than 1 Plegridy prefilled syringe every 14 days.

How should I store Plegridy?

- Store Plegridy in the refrigerator between 36°F to 46°F (2°C to 8°C).
- If a refrigerator is not available, Plegridy may be stored at room temperature up to 77°F (25°C) for a total of 30 days.
- You can store your Plegridy prefilled syringes at room temperature and then put it back in the refrigerator.
- Do not freeze Plegridy. Do not use Plegridy that has been frozen.
- Store Plegridy in the original carton to protect it from light.

Keep the Plegridy prefilled syringe and all medicines out of the reach of children.

Supplies you will need for the Plegridy injection:

- 1 Plegridy Administration Dose Pack that contains:
  - 1 Plegridy prefilled syringe
  - 23 gauge, 1¼ inch long sterile needle

Additional supplies not included in your Plegridy Administration Dose pack:

- 1 alcohol wipe
- 1 gauze pad
- 1 adhesive bandage
- a sharps disposal container for throwing away used syringes and needles. See “After the Plegridy injection” at the end of these instructions.

Preparing the dose of Plegridy:

- Find a well-lit, clean, flat work surface like a table and collect all the supplies you will need to give yourself or receive an injection.
- Take 1 Plegridy Administration Dose Pack out of the refrigerator and let it come to room temperature for about 30 minutes. Do not use external heat sources such as hot water to warm the Plegridy prefilled syringe.
- Check the expiration date printed on the Plegridy prefilled syringe, Plegridy Administration Dose Pack, and the outer carton. Do not use the Plegridy prefilled syringe past the expiration date.
- Wash your hands with soap and water.

Identifying parts of the Plegridy prefilled syringe (See Figure A).

Preparing the Plegridy injection:

Step 1: Check the Plegridy prefilled syringe (See Figure A):

- The syringe should not have any cracks or damage.
- Check that the cap is intact and has not been removed.
- Plegridy should look slightly clear, colorless to slightly yellow, and should not have any particles in it.

Do not use the Plegridy prefilled syringe if:

- the syringe is cracked or damaged.
- the solution is cloudy, colored other than slightly yellow, or has lumps or particles in it.
- the cap has been removed or is not tightly attached.

If you cannot use that syringe, you will need to get a new syringe. Contact Biogen at 1-800-456-2255.

Step 2: With 1 hand, hold the Plegridy prefilled syringe right under the cap and with the cap pointing up (See Figure B).

- Make sure you are holding the Plegridy prefilled syringe by the ridged part, directly under the cap.

Step 3: With the other hand, grasp the cap and bend it at a 90º angle until the cap snaps off (See Figure C and Figure D).

Step 4: Open the sterile needle package and take out the covered needle. Hold the Plegridy prefilled syringe with the glass syringe tip pointing up. Press the needle on the Plegridy prefilled syringe glass tip (See Figure E).

Step 5: Gently turn the needle to the right (clockwise) until it is tight and firmly attached (See Figure F).

- If the needle is not firmly attached, it may leak and you may not get your full dose of Plegridy.
- Do not remove the protective cover from the needle.

Giving the Plegridy injection:

- Your healthcare provider should show you or a caregiver how to prepare and inject the dose of Plegridy before the Plegridy prefilled syringe is used for the first time. Your healthcare provider should watch you inject the dose of Plegridy the first time the Plegridy prefilled syringe is used.
- Inject your Plegridy exactly as your healthcare provider has shown you.
- Plegridy is injected into the muscle (intramuscularly).
- Plegridy should be injected into the thigh (See Figure G).
- Change (rotate) your injection sites for each dose. Do not use the same injection site for each injection.
- Do not inject into an area of the body where the skin is irritated, reddened, bruised, infected or scarred in any way.

Step 6: Choose your left or right thigh and wipe the skin with an alcohol wipe (See Figure G). Let the injection site dry before injecting the dose.

- Do not touch this area again before giving the injection.

Step 7: Pull the protective cover straight off the needle (See Figure H). Do not twist the cover off.

Step 8: With 1 hand, stretch the skin out around the injection site. With the other hand, hold the syringe like a pencil. Use a quick dart-like motion and insert the needle at a 90º angle, through the skin and into the muscle (See Figure I). After the needle is in, let go of the skin.

Step 9: Slowly push the plunger down until the syringe is empty (See Figure J).

Step 10: Pull the needle out of the skin (See Figure K). Press down on the injection site with the gauze pad for a few seconds or rub gently in a circular motion.

- If you see blood after you press the injection site for a few seconds, wipe it off with the gauze pad and apply an adhesive bandage.

After the Plegridy injection:

- Do not recap the needle. Recapping the needle can lead to a needle stick injury.
- Put your used needles and syringes in a FDA-cleared sharps disposal container right away after use. Do not throw away (dispose of) loose needles and syringes in your household trash.
- If you do not have a FDA-cleared sharps disposal container, you may use a household container that is:
  - made of heavy-duty plastic,
  - can be closed with a tight-fitting puncture-resistant lid, without sharps being able to come out,
  - upright and stable during use,
  - leak-resistant, and
  - properly labeled to warn of hazardous waste inside the container.
- When your sharps disposal container is almost full, you will need to follow your community guidelines for the right way to dispose of your sharps disposal container. There may be state or local laws about how you should throw away used needles and syringes. For more information about safe sharps disposal, and for specific information about sharps disposal in the state that you live in, go to the FDA's website at: http://www.fda.gov/safesharpsdisposal
- Do not dispose of your used sharps disposal container in your household trash unless your community guidelines permit this. Do not recycle your used sharps disposal container.

Check your injection site:

- After 2 hours, check the injection site for redness, pain, itching, swelling, tenderness, a break in your skin that becomes blue and black, or drains fluid. If you have a skin reaction and it does not clear up in a few days, contact your healthcare provider.

General information about the safe and effective use of Plegridy

- Always use a new Plegridy prefilled syringe and needle for each injection. Do not re-use your Plegridy prefilled syringe or needles.
- Do not share your Plegridy prefilled syringe or needles.

Manufactured by:

Biogen Inc.

Cambridge, MA, 02142, USA

U.S. License # 1697

©Biogen Inc. [2021]. All rights reserved.

1-800-456-2255

This Instructions for Use has been approved by the U.S. Food and Drug Administration.

Issued: 1/2021

54927-01

Instructions for Use

PLEGRIDY® (PLEGG-rih-dee)

(peginterferon beta-1a)

injection for intramuscular use

Titration Kit for use with the PLEGRIDY intramuscular Single-Dose Prefilled Syringe Only

Read this Instructions for Use before you start using Plegridy and each time you get a refill. There may be new information. This information does not take the place of talking to your healthcare provider about your medical condition or your treatment.

Important information: The tip of the cap of the Plegridy prefilled syringe is made of natural rubber latex. Tell your healthcare provider if you are allergic to rubber or latex.

Note:

- Before you use your Plegridy prefilled syringe for the first time, your healthcare provider should show you or your caregiver how to prepare and inject your Plegridy prefilled syringe the right way.
- Each Plegridy prefilled syringe can be used 1 time only. Do not share your Plegridy prefilled syringe with anyone else. By sharing the needle, you may give an infection to them or get an infection from them.
- Do not use more than 1 Plegridy prefilled syringe every 14 days.

How should I store Plegridy?

- Store Plegridy in the refrigerator between 36°F to 46°F (2°C to 8°C).
- If a refrigerator is not available, Plegridy may be stored at room temperature up to 77°F (25°C) for a total of 30 days.
  - You can store your Plegridy prefilled syringes at room temperature and then put it back in the refrigerator.
- Do not freeze Plegridy. Do not use Plegridy that has been frozen.
- Store Plegridy in the original carton to protect it from light.

Keep the Plegridy Titration Kit, the Plegridy prefilled syringe, and all medicines out of the reach of children.

Supplies you will need for the Plegridy injection:

- 1 Plegridy Titration Kit that contains:
  - 1 yellow clip
  - 1 purple clip
- 1 Plegridy Administration Dose Pack that contains:
  - 1 Plegridy prefilled syringe
  - 23 gauge, 1¼ inch long sterile needle

Additional supplies not included in your Plegridy Titration Kit and Plegridy Administration Dose Pack:

- 1 alcohol wipe
- 1 gauze pad
- 1 adhesive bandage
- a sharps disposal container for throwing away used syringes and needles. See “After the Plegridy injection” at the end of these instructions.

Preparing the Plegridy Prefilled Syringe:

- Find a well-lit, clean, flat work surface like a table and collect all the supplies you will need to give yourself or receive an injection.
- Take 1 Plegridy Administration Dose Pack out of the refrigerator and let it come to room temperature for about 30 minutes. Do not use external heat sources such as hot water to warm the Plegridy prefilled syringe.
- Check the expiration date printed on the Plegridy prefilled syringe, Plegridy prefilled syringe Administration Dose Package carton, and the outer carton. Do not use the Plegridy prefilled syringe past the expiration date.
- Wash your hands with soap and water.

Identifying parts of the Plegridy prefilled syringe (See Figure A).

Preparing the Plegridy injection:

Step 1: Check the Plegridy prefilled syringe (Figure A):

- The syringe should not have any cracks or damage.
- Check that the cap is intact and has not been removed.
- Plegridy should look slightly clear, colorless to slightly yellow, and should not have any particles in it.
- Do not use the Plegridy prefilled syringe if:
  - the syringe is cracked or damaged.
  - the solution is cloudy, colored other than slightly yellow, or has lumps or particles in it.
  - the cap has been removed or is not tightly attached.

If you cannot use that syringe, you will need to get a new
syringe. Contact Biogen at 1-800-456-2255.

Step 2: With 1 hand, hold the Plegridy prefilled syringe right under the cap and with the cap pointing up (See Figure B).

- Make sure you are holding the Plegridy prefilled syringe by the ridged part, directly under the cap.

Step 3: With the other hand, grasp the cap and bend it at a 90º angle until the cap snaps off (See Figure C and Figure D).

Step 4: Open the sterile needle package and take out the covered needle. Hold the Plegridy prefilled syringe with the glass syringe tip pointing up. Press the needle on the Plegridy prefilled syringe glass tip (See Figure E).

Step 5: Gently turn the needle to the right (clockwise) until it is tight and firmly attached (See Figure F).

- If the needle is not firmly attached, it may leak and you may not get your full dose of Plegridy.
- Do not remove the protective cover from the needle.

Using the Plegridy prefilled syringe with the Plegridy Titration Kit:

- You must prepare the Plegridy prefilled syringe and needle before you put it into the Plegridy titration clip. Follow Step 1 to Step 5 above to prepare the Plegridy prefilled syringe.
- Your Plegridy dose may be titrated over 2 doses by using the Plegridy prefilled syringe with the Plegridy Titration Kit.
  - Dose 1 (Day 1): ½ dose (yellow clip)
  - Dose 2 (Day 15): ¾ dose (purple clip)
  - Dose 3 (Day 29): a full dose (no clip needed)
- The 2 Plegridy titration clips are for single-use only with the Plegridy prefilled syringe. Do not re-use the Plegridy prefilled syringe or Plegridy titration clips.

Identifying the parts of Plegridy Titration Kit (See Figure G):

- The Plegridy titration clip has a “collar” on top that will stop the syringe from injecting a full dose (See Figure H). The “collar” is to make sure that you receive the correct dose.

Attaching the Plegridy titration clip:

Step 6: Choose the right titration clip for your dose.

- Dose 1 (Day 1): Choose the yellow clip to give ½ dose (See Figure I).
- Dose 2 (Day 15): Choose the purple clip to give ¾ dose (See Figure J).

Step 7: Put the correct titration clip on a flat surface with the door open (See Figure K).

Step 8: Line up the Plegridy prefilled syringe over the titration clip with the plunger pointing to the left and the needle pointing to the right (See Figure L).

Step 9: Push the Plegridy prefilled syringe down into the titration clip until both ends “snap” into place (See Figure M).

Step 10: Using 2 fingers, push the door down until it closes over the Plegridy prefilled syringe (See Figure N).

- You will hear a “snap” when the door is closed the right way. Do not open door after it is closed.

Step 11: Check to make sure that the Plegridy prefilled syringe is in the titration clip the right way and that the door is tightly closed.

Giving the Plegridy injection:

- Your healthcare provider should show you or a caregiver how to prepare and inject the dose of Plegridy before the Plegridy prefilled syringe is used for the first time. Your healthcare provider should watch you inject the dose of Plegridy the first time the Plegridy prefilled syringe is used.
- Inject your Plegridy exactly as your healthcare provider has shown you.
- Plegridy is injected into the muscle (intramuscularly).
- Plegridy should be injected into the thigh (See Figure P).
- Change (rotate) your injection sites for each dose. Do not use the same injection site for each injection.
- Do not inject into an area of the body where the skin is irritated, reddened, bruised, infected or scarred in any way.

Step 12: Choose your left or right thigh and wipe the skin with an alcohol wipe (See Figure P). Let the injection site dry before injecting the dose.

- Do not touch this area again before giving the injection.

Step 13: Pull the protective cover straight off the needle (See Figure Q). Do not twist the cover off.

Step 14: With 1 hand, stretch the skin out around the injection site. With the other hand, hold the syringe like a pencil. Use a quick dart-like motion and insert the needle at a 90º angle, through the skin and into the muscle (See Figure R). After the needle is in, let go of the skin.

Step 15: Slowly push the plunger all the way down until it touches the collar (See Figure S).

Step 16: Pull the needle out of the skin (See Figure T). Press down on the injection site with the gauze pad for a few seconds or rub gently in a circular motion.

- If you see blood after you press the injection site for a few seconds, wipe it off with the gauze pad and apply an adhesive bandage.

After the Plegridy injection:

- Do not recap the needle. Recapping the needle can lead to a needle stick injury.
- Put your used needles and syringes in a FDA-cleared sharps disposal container right away after use. Do not throw away (dispose of) loose needles and syringes in your household trash.
- If you do not have a FDA-cleared sharps disposal container, you may use a household container that is:
  - made of heavy-duty plastic,
  - can be closed with a tight-fitting puncture-resistant lid, without sharps being able to come out,
  - upright and stable during use,
  - leak-resistant, and
  - properly labeled to warn of hazardous waste inside the container.
- When your sharps disposal container is almost full, you will need to follow your community guidelines for the right way to dispose of your sharps disposal container. There may be state or local laws about how you should throw away used needles and syringes. For more information about safe sharps disposal, and for specific information about sharps disposal in the state that you live in, go to the FDA's website at: http://www.fda.gov/safesharpsdisposal
- Do not dispose of your used sharps disposal container in your household trash unless your community guidelines permit this. Do not recycle your used sharps disposal container.

Check the injection site:

- After 2 hours, check the injection site for redness, pain, itching, swelling, tenderness, a break in your skin that becomes blue and black, or drains fluid. If you have a skin reaction and it does not clear up in a few days, contact your healthcare provider.

General information about the safe and effective use of Plegridy

- Always use a new Plegridy prefilled syringe, titration clip, and needle. Do not re-use your Plegridy prefilled syringe, titration clip, or needle.
- Do not share your Plegridy prefilled syringe, titration clip, or needle.
- You can use the table below to keep track of your injections.

Day | Dose | Use Titration Clip | Date/Time
Day 1 | 1/2 Dose | Yellow
Day 15 | 3/4 Dose | Purple
Day 29 | Full Dose | None

Manufactured for:
Biogen Inc.
Cambridge, MA 02142 USA
©2021 Biogen Inc. All rights reserved.
1-800-456-2255
This Instructions for Use has been approved by the U.S. Food and Drug Administration.
Revised: 1/2021
54930-01

Principal Display Panel - Carton Label

NDC 64406-012-01

Plegridy-Pen

(peginterferon beta-1a)

Injection

63. mcg/0.5 mL

94 mcg/0.5 mL

For subcutaneous use only

Starter Pack

Contents:

Dose 1: 1 Single-Dose 63 mcg/0.5 mL
Prefilled Autoinjector

Dose 2: 1 Single-Dose 94 mcg/0.5 mL
Prefilled Autoinjector

Dispense with enclosed Medicaton Guide

Rx Only

Biogen®

Principal Display Panel - Carton Label

NDC 64406-011-01

Plegridy TMPen

(peginterferon beta-1a)
Injection

125 mcg/0.5 mL

For subcutaneous use only

Every 14 Days

Contents: 2 Single-Dose Prefilled Autoinjectors

Dispense with enclosed Medication Guide

Rx only

Biogen®

Principal Display Panel - Carton Label

NDC 64406-016-01

Plegridy™

(peginterferon beta-1a)
Injection

63 mcg/0.5 mL

94 mcg/0.5 mL

For subcutaneous use only

Starter Pack

Contents:

Dose 1: 1 Single-Dose 63 mcg/0.5 mL
Prefilled Syringe

Dose 2: 1 Single-Dose 94 mcg/0.5 mL
Prefilled Syringe

Rx only

Dispense with enclosed
Medication Guide

Biogen®

Principal Display Panel - Carton Label

NDC 64406-015-01

Plegridy TM

(peginterferon beta-1a)
Injection

125 mcg/0.5 mL

For subcutaneous use only

Every 14 Days

Contents:

2 Single-Dose Prefilled Syringes

Rx only

Dispense with enclosed
Medication Guide

Biogen®

Principal Display Panel –Carton Label

NDC 64406-017-01

Plegridy®
(peginterferon beta-1a)
Injection

125 mcg/0.5 mL

For intramuscular use only

Every 14 Days

Contents:

2 Single-Dose Prefilled Syringes and
2 Needles for Injection

Every 14 Days

Dispense with enclosed
Medication Guide

Rx only